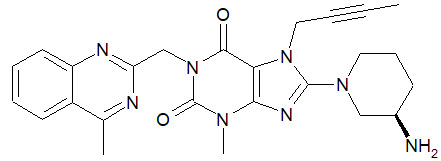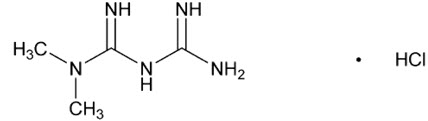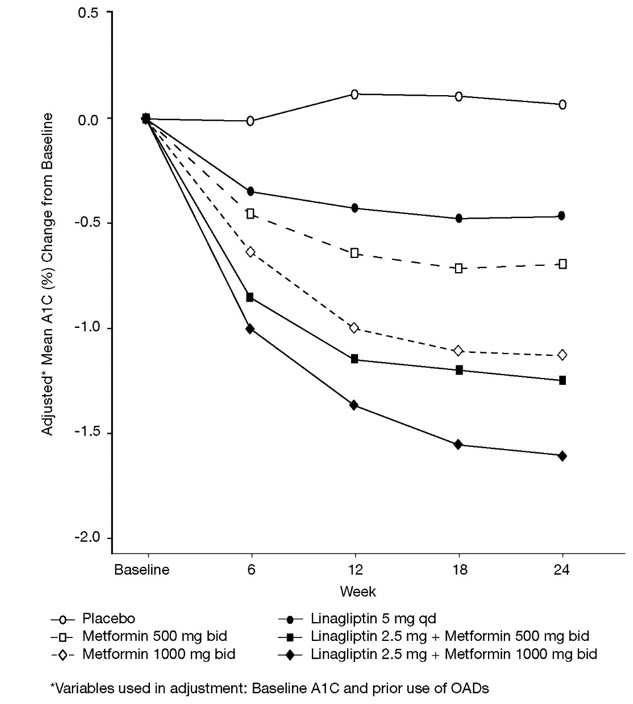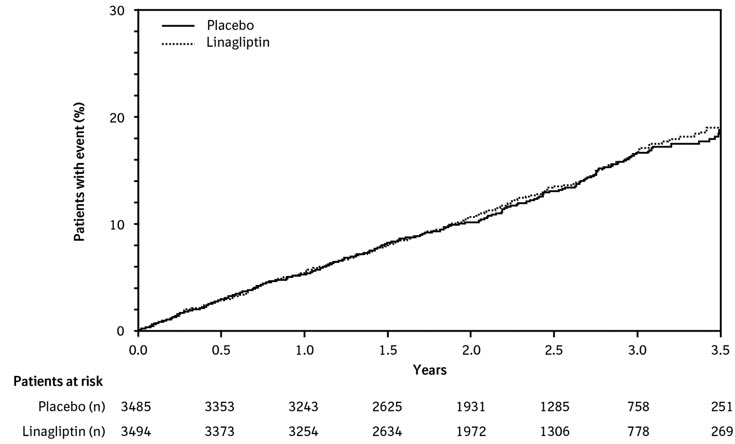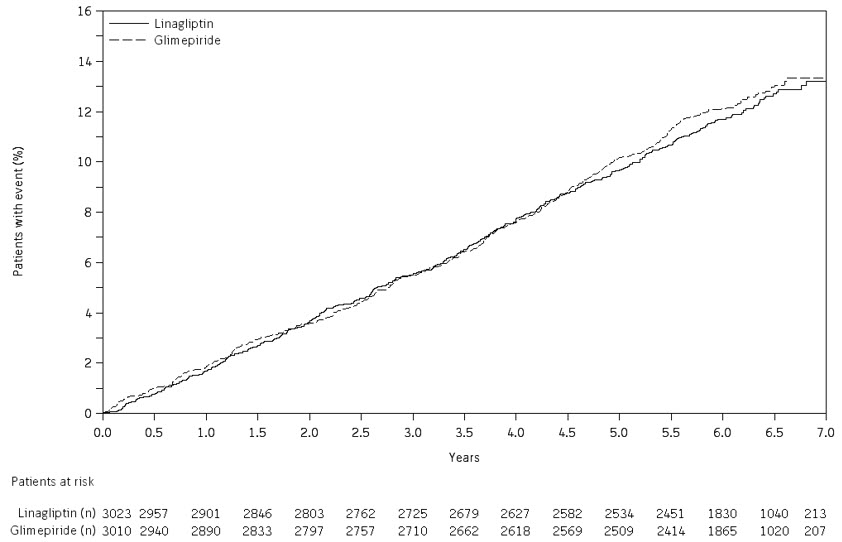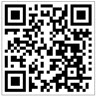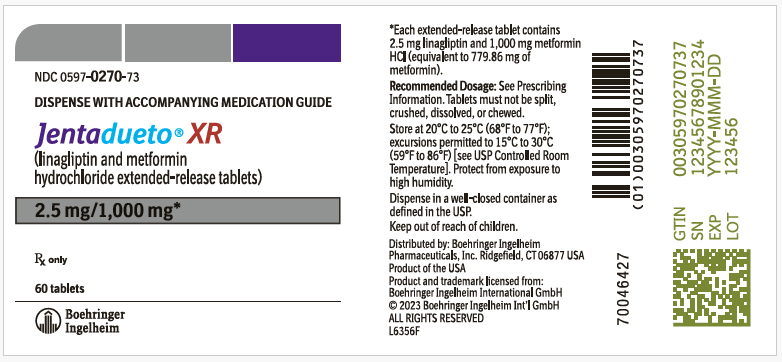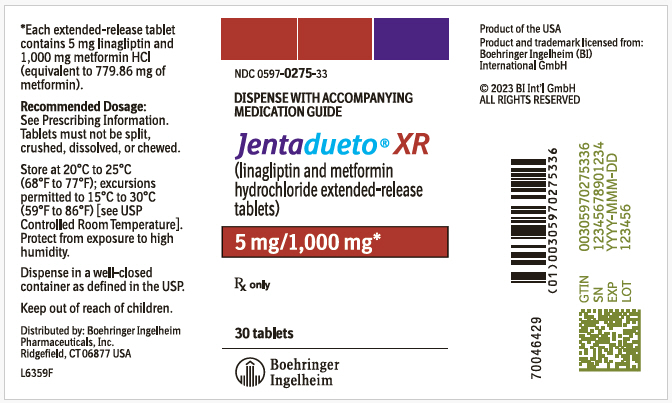 DRUG LABEL: Jentadueto XR
NDC: 0597-0270 | Form: TABLET, FILM COATED, EXTENDED RELEASE
Manufacturer: Boehringer Ingelheim Pharmaceuticals, Inc.
Category: prescription | Type: HUMAN PRESCRIPTION DRUG LABEL
Date: 20240524

ACTIVE INGREDIENTS: LINAGLIPTIN 2.5 mg/1 1; METFORMIN HYDROCHLORIDE 1000 mg/1 1

HIGHLIGHTS OF PRESCRIBING INFORMATION

These highlights do not include all the information needed to use JENTADUETO XR safely and effectively. See full prescribing information for JENTADUETO XR.
JENTADUETO® XR (linagliptin and metformin hydrochloride extended-release tablets), for oral use
Initial U.S. Approval: 2012

WARNING: LACTIC ACIDOSIS

See full prescribing information for complete boxed warning.

- Postmarketing cases of metformin-associated lactic acidosis have resulted in death, hypothermia, hypotension, and resistant bradyarrhythmias. Symptoms included malaise, myalgias, respiratory distress, somnolence, and abdominal pain. Laboratory abnormalities included elevated blood lactate levels, anion gap acidosis, increased lactate/pyruvate ratio; and metformin plasma levels generally >5 mcg/mL. (5.1)
- Risk factors include renal impairment, concomitant use of certain drugs, age ≥65 years old, radiological studies with contrast, surgery and other procedures, hypoxic states, excessive alcohol intake, and hepatic impairment. Steps to reduce the risk of and manage metformin-associated lactic acidosis in these high risk groups are provided in the Full Prescribing Information. (5.1)
- If lactic acidosis is suspected, discontinue JENTADUETO XR and institute general supportive measures in a hospital setting. Prompt hemodialysis is recommended. (5.1)

1 INDICATIONS AND USAGE

JENTADUETO XR is a combination of linagliptin, a dipeptidyl peptidase-4 (DPP-4) inhibitor and metformin hydrochloride (HCl), a biguanide, indicated as an adjunct to diet and exercise to improve glycemic control in adults with type 2 diabetes mellitus (1)

Limitations of Use

- Not recommended in patients with type 1 diabetes mellitus (1)
- Has not been studied in patients with a history of pancreatitis (1)

2 DOSAGE AND ADMINISTRATION

- Individualize the starting dosage of JENTADUETO XR based on the patient's current regimen (2.1)
- The maximum recommended dosage is 5 mg linagliptin/2,000 mg metformin HCl once daily (2.1)
- Take orally once daily with a meal, with gradual dose escalation to reduce the gastrointestinal effects due to metformin (2.1)
- Swallow whole; do not split, crush, dissolve, or chew (2.1)
- Prior to initiation, assess renal function with estimated glomerular filtration rate (eGFR) (2.2)
  - Do not use in patients with eGFR below 30 mL/min/1.73 m^2
  - Initiation is not recommended in patients with eGFR between 30 - 45 mL/min/1.73 m^2
  - Assess risk/benefit of continuing if eGFR falls below 45 mL/min/1.73 m^2
  - Discontinue if eGFR falls below 30 mL/min/1.73 m^2
- JENTADUETO XR may need to be discontinued at time of, or prior to, iodinated contrast imaging procedures (2.3)

3 DOSAGE FORMS AND STRENGTHS

Tablets:

5 mg linagliptin/1,000 mg metformin HCl extended-release (3)

2.5 mg linagliptin/1,000 mg metformin HCl extended-release (3)

4 CONTRAINDICATIONS

- Severe renal impairment (eGFR below 30 mL/min/1.73 m^2) (4)
- Metabolic acidosis, including diabetic ketoacidosis (4)
- Hypersensitivity to linagliptin, metformin, or any of the excipients in JENTADUETO XR (4)

5 WARNINGS AND PRECAUTIONS

- Lactic acidosis: See boxed warning (5.1)
- Pancreatitis: There have been reports of acute pancreatitis, including fatal pancreatitis. If pancreatitis is suspected, promptly discontinue JENTADUETO XR. (5.2)
- Hypoglycemia: Consider lowering the dosage of insulin secretagogue or insulin to reduce the risk of hypoglycemia when initiating JENTADUETO XR. (5.3)
- Hypersensitivity reactions: Serious hypersensitivity reactions (e.g., anaphylaxis, angioedema, and exfoliative skin conditions) have occurred with JENTADUETO XR. If hypersensitivity reactions occur discontinue JENTADUETO XR, treat promptly, and monitor until signs and symptoms resolve. (5.4)
- Vitamin B12 deficiency: Metformin may lower vitamin B12 levels. Measure hematologic parameters annually and vitamin B12 at 2 to 3 year intervals and manage any abnormalities. (5.5)
- Arthralgia: Severe and disabling arthralgia has been reported in patients taking linagliptin. Consider as a possible cause for severe joint pain and discontinue drug if appropriate. (5.6)
- Bullous pemphigoid: There have been reports of bullous pemphigoid requiring hospitalization. Tell patients to report development of blisters or erosions. If bullous pemphigoid is suspected, discontinue JENTADUETO XR. (5.7)
- Heart failure: Heart failure has been observed with two other members of the DPP-4 inhibitor class. Consider risks and benefits of JENTADUETO XR in patients who have known risk factors for heart failure. Monitor for signs and symptoms. (5.8)

6 ADVERSE REACTIONS

Most common adverse reactions (incidence ≥5% and more often than placebo) were nasopharyngitis and diarrhea (6.1)

To report SUSPECTED ADVERSE REACTIONS, contact Boehringer Ingelheim Pharmaceuticals, Inc. at 1-800-542-6257 or FDA at 1-800-FDA-1088 or www.fda.gov/medwatch.

7 DRUG INTERACTIONS

- Carbonic Anhydrase Inhibitors: May increase risk of lactic acidosis. Consider more frequent monitoring. (7)
- Drugs that Reduce Metformin Clearance: May increase risk of lactic acidosis. Consider benefits and risks of concomitant use. (7)
- Alcohol: Can potentiate the effect of metformin on lactate metabolism. Warn patients against excessive alcohol intake. (7)
- Strong P-glycoprotein/CYP3A4 Inducer: Efficacy may be reduced when administered in combination (e.g., rifampin). Use of alternative treatments is strongly recommended. (7)

8 USE IN SPECIFIC POPULATIONS

- Females and Males of Reproductive Potential: Advise premenopausal females of the potential for an unintended pregnancy (8.3)
- Geriatric Use: Assess renal function more frequently (8.5)
- Hepatic Impairment: Avoid use in patients with hepatic impairment (8.7)

FULL PRESCRIBING INFORMATION

WARNING: LACTIC ACIDOSIS

Postmarketing cases of metformin-associated lactic acidosis have resulted in death, hypothermia, hypotension, and resistant bradyarrhythmias. The onset of metformin-associated lactic acidosis is often subtle, accompanied only by nonspecific symptoms such as malaise, myalgias, respiratory distress, somnolence, and abdominal pain. Metformin-associated lactic acidosis was characterized by elevated blood lactate levels (>5 mmol/Liter), anion gap acidosis (without evidence of ketonuria or ketonemia), an increased lactate/pyruvate ratio; and metformin plasma levels generally >5 mcg/mL [see Warnings and Precautions (5.1)].

Risk factors for metformin-associated lactic acidosis include renal impairment, concomitant use of certain drugs (e.g., carbonic anhydrase inhibitors such as topiramate), age 65 years old or greater, having a radiological study with contrast, surgery and other procedures, hypoxic states (e.g., acute congestive heart failure), excessive alcohol intake, and hepatic impairment.

Steps to reduce the risk of and manage metformin-associated lactic acidosis in these high risk groups are provided in the full prescribing information [see Dosage and Administration (2.2), Contraindications (4), Warnings and Precautions (5.1), Drug Interactions (7), and Use in Specific Populations (8.6, 8.7)].

If metformin-associated lactic acidosis is suspected, immediately discontinue JENTADUETO XR and institute general supportive measures in a hospital setting. Prompt hemodialysis is recommended [see Warnings and Precautions (5.1)].

1 INDICATIONS AND USAGE

JENTADUETO XR is indicated as an adjunct to diet and exercise to improve glycemic control in adults with type 2 diabetes mellitus.

Limitations of Use

JENTADUETO XR is not recommended in patients with type 1 diabetes mellitus.

JENTADUETO XR has not been studied in patients with a history of pancreatitis. It is unknown whether patients with a history of pancreatitis are at an increased risk for the development of pancreatitis while using JENTADUETO XR [see Warnings and Precautions (5.2)].

2 DOSAGE AND ADMINISTRATION

2.1 Recommended Dosage and Administration

The dosage of JENTADUETO XR should be individualized on the basis of both effectiveness and tolerability, while not exceeding the maximum recommended total daily dosage of linagliptin 5 mg and metformin hydrochloride (HCl) 2,000 mg. JENTADUETO XR should be given orally once daily with a meal. Dosage escalation should be gradual to reduce the gastrointestinal (GI) side effects associated with metformin use.

Recommended starting dosage:

- In patients currently not treated with metformin HCl, initiate JENTADUETO XR treatment with 5 mg linagliptin/1,000 mg metformin HCl extended-release once daily with a meal.
- In patients already treated with metformin HCl, start JENTADUETO XR with 5 mg of linagliptin total daily dosage and a similar total daily dosage of metformin HCl once daily with a meal.
- In patients already treated with linagliptin and metformin HCl or JENTADUETO, switch to JENTADUETO XR containing 5 mg of linagliptin total daily dosage and a similar total daily dosage of metformin HCl once daily with a meal.

JENTADUETO XR should be swallowed whole. The tablets must not be split, crushed, dissolved, or chewed.

JENTADUETO XR 5 mg linagliptin/1,000 mg metformin HCl extended-release tablet should be taken as a single tablet once daily. Patients using 2.5 mg linagliptin/1,000 mg metformin HCl extended-release tablets should take two tablets together once daily.

2.2 Recommended Dosing in Renal Impairment

Assess renal function prior to initiation of JENTADUETO XR and periodically thereafter.

JENTADUETO XR is contraindicated in patients with an estimated glomerular filtration rate (eGFR) below 30 mL/min/1.73 m^2.

Initiation of JENTADUETO XR in patients with an eGFR between 30-45 mL/min/1.73 m^2 is not recommended.

In patients taking JENTADUETO XR whose eGFR later falls below 45 mL/min/1.73 m^2, assess benefit/risk of continuing therapy.

Discontinue JENTADUETO XR if the patient's eGFR later falls below 30 mL/min/1.73 m^2 [see Contraindications (4) and Warnings and Precautions (5.1)].

2.3 Discontinuation for Iodinated Contrast Imaging Procedures

Discontinue JENTADUETO XR at the time of, or prior to, an iodinated contrast imaging procedure in patients with an eGFR between 30 and 60 mL/min/1.73 m^2; in patients with a history of liver disease, alcoholism or heart failure; or in patients who will be administered intra-arterial iodinated contrast. Re-evaluate eGFR 48 hours after the imaging procedure; restart JENTADUETO XR if renal function is stable [see Warnings and Precautions (5.1)].

3 DOSAGE FORMS AND STRENGTHS

JENTADUETO XR tablets are a combination of linagliptin and extended-release metformin HCl available as:

- 5 mg/1,000 mg are white, oval-shaped coated tablets with one side printed in black ink with the Boehringer Ingelheim symbol and "D5" on the top line and "1000 M" on the bottom line.
- 2.5 mg/1,000 mg are yellow, oval-shaped coated tablets with one side printed in black ink with the Boehringer Ingelheim symbol and "D2" on the top line and "1000 M" on the bottom line.

4 CONTRAINDICATIONS

JENTADUETO XR is contraindicated in patients with:

- severe renal impairment (eGFR below 30 mL/min/1.73 m^2) [see Warnings and Precautions (5.1)].
- acute or chronic metabolic acidosis, including diabetic ketoacidosis [see Warnings and Precautions (5.1)].
- hypersensitivity to linagliptin, metformin, or any of the excipients in JENTADUETO XR, reactions such as anaphylaxis, angioedema, exfoliative skin conditions, urticaria, or bronchial hyperreactivity have occurred with linagliptin [see Warnings and Precautions (5.4) and Adverse Reactions (6.1)].

5 WARNINGS AND PRECAUTIONS

5.1 Lactic Acidosis

Metformin

There have been postmarketing cases of metformin-associated lactic acidosis, including fatal cases. These cases had a subtle onset and were accompanied by nonspecific symptoms such as malaise, myalgias, abdominal pain, respiratory distress, or increased somnolence; however, hypothermia, hypotension and resistant bradyarrhythmias have occurred with severe acidosis. Metformin-associated lactic acidosis was characterized by elevated blood lactate concentrations (>5 mmol/Liter), anion gap acidosis (without evidence of ketonuria or ketonemia), and an increased lactate:pyruvate ratio; metformin plasma levels generally >5 mcg/mL. Metformin decreases liver uptake of lactate increasing lactate blood levels which may increase risk of lactic acidosis, especially in patients at risk.

If metformin-associated lactic acidosis is suspected, general supportive measures should be instituted promptly in a hospital setting, along with immediate discontinuation of JENTADUETO XR. In JENTADUETO XR-treated patients with a diagnosis or strong suspicion of lactic acidosis, prompt hemodialysis is recommended to correct the acidosis and remove accumulated metformin (metformin is dialyzable, with clearance of up to 170 mL/min under good hemodynamic conditions). Hemodialysis has often resulted in reversal of symptoms and recovery.

Educate patients and their families about the symptoms of lactic acidosis and if these symptoms occur instruct them to discontinue JENTADUETO XR and report these symptoms to their healthcare provider.

For each of the known and possible risk factors for metformin-associated lactic acidosis, recommendations to reduce the risk of and manage metformin-associated lactic acidosis are provided below:

Renal Impairment: The postmarketing metformin-associated lactic acidosis cases primarily occurred in patients with significant renal impairment. The risk of metformin accumulation and metformin-associated lactic acidosis increases with the severity of renal impairment because metformin is substantially excreted by the kidney. Clinical recommendations based upon the patient's renal function include [see Dosage and Administration (2.2) and Clinical Pharmacology (12.3)]:

- Before initiating JENTADUETO XR, obtain an estimated glomerular filtration rate (eGFR).
- JENTADUETO XR is contraindicated in patients with an eGFR less than 30 mL/min/1.73 m^2 [see Contraindications (4)].
- Initiation of JENTADUETO XR is not recommended in patients with eGFR between 30 – 45 mL/min/1.73 m^2.
- Obtain an eGFR at least annually in all patients taking JENTADUETO XR. In patients at increased risk for the development of renal impairment (e.g., the elderly), renal function should be assessed more frequently.
- In patients taking JENTADUETO XR whose eGFR later falls below 45 mL/min/1.73 m^2, assess the benefit and risk of continuing therapy.

Drug Interactions: The concomitant use of JENTADUETO XR with specific drugs may increase the risk of metformin-associated lactic acidosis: those that impair renal function, result in significant hemodynamic change, interfere with acid-base balance or increase metformin accumulation [see Drug Interactions (7)]. Therefore, consider more frequent monitoring of patients.

Age 65 or Greater: The risk of metformin-associated lactic acidosis increases with the patient's age because elderly patients have a greater likelihood of having hepatic, renal, or cardiac impairment than younger patients. Assess renal function more frequently in elderly patients [see Use in Specific Populations (8.5)].

Radiological Studies with Contrast: Administration of intravascular iodinated contrast agents in metformin-treated patients has led to an acute decrease in renal function and the occurrence of lactic acidosis. Stop JENTADUETO XR at the time of, or prior to, an iodinated contrast imaging procedure in patients with an eGFR between 30 and 60 mL/min/1.73 m^2; in patients with a history of hepatic impairment, alcoholism, or heart failure; or in patients who will be administered intra-arterial iodinated contrast. Re-evaluate eGFR 48 hours after the imaging procedure, and restart JENTADUETO XR if renal function is stable.

Surgery and Other Procedures: Withholding of food and fluids during surgical or other procedures may increase the risk for volume depletion, hypotension and renal impairment. JENTADUETO XR should be temporarily discontinued while patients have restricted food and fluid intake.

Hypoxic States: Several of the postmarketing cases of metformin-associated lactic acidosis occurred in the setting of acute congestive heart failure (particularly when accompanied by hypoperfusion and hypoxemia). Cardiovascular collapse (shock), acute myocardial infarction, sepsis, and other conditions associated with hypoxemia have been associated with lactic acidosis and may also cause prerenal azotemia. When such events occur, discontinue JENTADUETO XR.

Excessive Alcohol Intake: Alcohol potentiates the effect of metformin on lactate metabolism and this may increase the risk of metformin-associated lactic acidosis. Warn patients against excessive alcohol intake while receiving JENTADUETO XR.

Hepatic Impairment: Patients with hepatic impairment have developed cases of metformin-associated lactic acidosis. This may be due to impaired lactate clearance resulting in higher lactate blood levels. Therefore, avoid use of JENTADUETO XR in patients with clinical or laboratory evidence of hepatic disease.

5.2 Pancreatitis

Acute pancreatitis, including fatal pancreatitis, has been reported in patients treated with linagliptin. In the CARMELINA trial [see Clinical Studies (14.2)], acute pancreatitis was reported in 9 (0.3%) patients treated with linagliptin and in 5 (0.1%) patients treated with placebo. Two patients treated with linagliptin in the CARMELINA trial had acute pancreatitis with a fatal outcome. There have been postmarketing reports of acute pancreatitis, including fatal pancreatitis, in patients treated with linagliptin.

Take careful notice of potential signs and symptoms of pancreatitis. If pancreatitis is suspected, promptly discontinue JENTADUETO XR and initiate appropriate management. It is unknown whether patients with a history of pancreatitis are at increased risk for the development of pancreatitis while using JENTADUETO XR.

5.3 Hypoglycemia with Concomitant Use with Insulin and Insulin Secretagogues

Insulin secretagogues and insulin are known to cause hypoglycemia. The risk of hypoglycemia is increased when JENTADUETO XR is used in combination with an insulin secretagogue (e.g., sulfonylurea) or insulin [see Adverse Reactions (6.1)]. Therefore, a lower dosage of the insulin secretagogue or insulin may be required to reduce the risk of hypoglycemia when used in combination with JENTADUETO XR.

5.4 Hypersensitivity Reactions

There have been postmarketing reports of serious hypersensitivity reactions in patients treated with linagliptin. These reactions include anaphylaxis, angioedema, and exfoliative skin conditions. Onset of these reactions occurred predominantly within the first 3 months after initiation of treatment with linagliptin, with some reports occurring after the first dose. If a serious hypersensitivity reaction is suspected, discontinue JENTADUETO XR, assess for other potential causes for the event, and institute alternative treatment for diabetes mellitus.

Angioedema has also been reported with other dipeptidyl peptidase-4 (DPP-4) inhibitors. Use caution in a patient with a history of angioedema to another DPP-4 inhibitor because it is unknown whether such patients will be predisposed to angioedema with JENTADUETO XR.

5.5 Vitamin B12 Deficiency

In metformin clinical trials of 29-week duration, a decrease to subnormal levels of previously normal serum vitamin B12 levels was observed in approximately 7% of metformin-treated patients. Such decrease, possibly due to interference with B12 absorption from the B12-intrinsic factor complex, may be associated with anemia but appears to be rapidly reversible with discontinuation of metformin or vitamin B12 supplementation. Certain individuals (those with inadequate vitamin B12 or calcium intake or absorption) appear to be predisposed to developing subnormal vitamin B12 levels. Measure hematologic parameters on an annual basis and vitamin B12 at 2 to 3 year intervals in patients on JENTADUETO XR and manage any abnormalities [see Adverse Reactions (6.1)].

5.6 Severe and Disabling Arthralgia

There have been postmarketing reports of severe and disabling arthralgia in patients taking linagliptin. The time to onset of symptoms following initiation of drug therapy varied from one day to years. Patients experienced relief of symptoms upon discontinuation of the medication. A subset of patients experienced a recurrence of symptoms when restarting the same drug or a different DPP-4 inhibitor. Consider DPP-4 inhibitors as a possible cause for severe joint pain and discontinue drug if appropriate.

5.7 Bullous Pemphigoid

Bullous pemphigoid was reported in 7 (0.2%) patients treated with linagliptin compared to none in patients treated with placebo in the CARMELINA trial [see Clinical Studies (14.2)], and 3 of these patients were hospitalized due to bullous pemphigoid. Postmarketing cases of bullous pemphigoid requiring hospitalization have been reported with DPP-4 inhibitor use. In reported cases, patients typically recovered with topical or systemic immunosuppressive treatment and discontinuation of the DPP-4 inhibitor. Tell patients to report development of blisters or erosions while receiving JENTADUETO XR. If bullous pemphigoid is suspected, JENTADUETO XR should be discontinued and referral to a dermatologist should be considered for diagnosis and appropriate treatment.

5.8 Heart Failure

An association between DPP-4 inhibitor treatment and heart failure has been observed in cardiovascular outcomes trials for two other members of the DPP-4 inhibitor class. These trials evaluated patients with type 2 diabetes mellitus and atherosclerotic cardiovascular disease.

Consider the risks and benefits of JENTADUETO XR prior to initiating treatment in patients at risk for heart failure, such as those with a prior history of heart failure and a history of renal impairment, and observe these patients for signs and symptoms of heart failure during therapy. Advise patients of the characteristic symptoms of heart failure and to immediately report such symptoms. If heart failure develops, evaluate and manage according to current standards of care and consider discontinuation of JENTADUETO XR.

6 ADVERSE REACTIONS

The following serious adverse reactions are described below or elsewhere in the prescribing information:

- Lactic Acidosis [see Warnings and Precautions (5.1)]
- Pancreatitis [see Warnings and Precautions (5.2)]
- Hypoglycemia with Concomitant Use with Insulin and Insulin Secretagogues [see Warnings and Precautions (5.3)]
- Hypersensitivity Reactions [see Warnings and Precautions (5.4)]
- Vitamin B12 Deficiency [see Warnings and Precautions (5.5)]
- Severe and Disabling Arthralgia [see Warnings and Precautions (5.6)]
- Bullous Pemphigoid [see Warnings and Precautions (5.7)]
- Heart Failure [see Warnings and Precautions (5.8)]

6.1 Clinical Trials Experience

Because clinical trials are conducted under widely varying conditions, adverse reaction rates observed in the clinical trials of a drug cannot be directly compared to rates in the clinical trials of another drug and may not reflect the rates observed in practice.

Linagliptin/Metformin

The safety of concomitantly administered linagliptin (daily dosage 5 mg) and metformin (mean daily dosage of approximately 1,800 mg) has been evaluated in 2,816 patients with type 2 diabetes mellitus treated for ≥12 weeks in clinical trials.

Three placebo-controlled trials with linagliptin + metformin were conducted: 2 studies were 24 weeks in duration, 1 trial was 12 weeks in duration. In the 3 placebo-controlled clinical studies, adverse reactions which occurred in ≥5% of patients receiving linagliptin + metformin (n=875) and were more common than in patients given placebo + metformin (n=539) included nasopharyngitis (5.7% vs 4.3%).

In a 24-week factorial design trial, adverse reactions reported in ≥5% of patients receiving linagliptin + metformin and were more common than in patients given placebo are shown in Table 1.

Table 1 Adverse Reactions Reported in ≥5% of Patients Treated with Linagliptin + Metformin and Greater than with Placebo in a 24-week Factorial-Design Trial
Adverse Reactions | Placebo (%) n=72 | Linagliptin Monotherapy (%) n=142 | Metformin Monotherapy (%) n=291 | Combination of Linagliptin with Metformin (%) n=286
Nasopharyngitis | 1.4 | 5.6 | 2.7 | 6.3
Diarrhea | 2.8 | 3.5 | 3.8 | 6.3

Other adverse reactions reported in clinical studies with treatment of linagliptin + metformin were hypersensitivity (e.g., urticaria, angioedema, or bronchial hyperreactivity), cough, decreased appetite, nausea, vomiting, pruritus, and pancreatitis.

Linagliptin

Adverse reactions reported in ≥2% of patients treated with linagliptin 5 mg and more commonly than in patients treated with placebo included: nasopharyngitis (7.0% vs 6.1%), diarrhea (3.3% vs 3.0%), and cough (2.1% vs 1.4%).

Rates for other adverse reactions for linagliptin 5 mg vs placebo when linagliptin was used in combination with specific antidiabetic agents were: urinary tract infection (3.1% vs 0%) and hypertriglyceridemia (2.4% vs 0%) when linagliptin was used as add-on to sulfonylurea; hyperlipidemia (2.7% vs 0.8%) and weight increased (2.3% vs 0.8%) when linagliptin was used as add-on to pioglitazone; and constipation (2.1% vs 1%) when linagliptin was used as add-on to basal insulin therapy.

Other adverse reactions reported in clinical studies with treatment of linagliptin monotherapy were hypersensitivity (e.g., urticaria, angioedema, localized skin exfoliation, or bronchial hyperreactivity) and myalgia. In the clinical trial program, pancreatitis was reported in 15.2 cases per 10,000 patient year exposure while being treated with linagliptin compared with 3.7 cases per 10,000 patient year exposure while being treated with comparator (placebo and active comparator, sulfonylurea). Three additional cases of pancreatitis were reported following the last administered dose of linagliptin.

Metformin

The most common (>5%) adverse reactions due to initiation of metformin therapy are diarrhea, nausea/vomiting, flatulence, abdominal discomfort, indigestion, asthenia, and headache.

In a 24-week clinical trial in which extended-release metformin or placebo was added to glyburide therapy, the most common (>5% and greater than placebo) adverse reactions in the combined treatment group were hypoglycemia (13.7% vs 4.9%), diarrhea (12.5% vs 5.6%), and nausea (6.7% vs 4.2%).

Other Adverse Reactions

Hypoglycemia

Linagliptin/Metformin

In a 24-week factorial design trial, hypoglycemia was reported in 4 (1.4%) of 286 subjects treated with linagliptin + metformin, 6 (2.1%) of 291 subjects treated with metformin, and 1 (1.4%) of 72 subjects treated with placebo. The incidence of hypoglycemia with plasma glucose <54 mg/dL was 8.1% in the linagliptin group (N=792) compared to 5.3% in the placebo group (N=263) when administered in combination with metformin and sulfonylurea in a 24-week trial.

Linagliptin

The incidence of severe hypoglycemia (requiring assistance) was 1.7% in the linagliptin group (N=631) compared to 1.1% in the placebo group (N=630) when administered in combination with basal insulin in a 52 week trial.

Laboratory Test Abnormalities in Clinical Trials of Linagliptin or Metformin

Linagliptin

Increase in Uric Acid: Changes in laboratory values that occurred more frequently in the linagliptin group and ≥1% more than in the placebo group were increases in uric acid (1.3% in the placebo group, 2.7% in the linagliptin group).

Increase in Lipase: In a placebo-controlled clinical trial with linagliptin in type 2 diabetes mellitus patients with micro- or macroalbuminuria, a mean increase of 30% in lipase concentrations from baseline to 24 weeks was observed in the linagliptin arm compared to a mean decrease of 2% in the placebo arm. Lipase levels above 3 times upper limit of normal were seen in 8.2% compared to 1.7% patients in the linagliptin and placebo arms, respectively.

Increase in Amylase: In a cardiovascular safety trial comparing linagliptin versus glimepiride in patients with type 2 diabetes mellitus, amylase levels above 3 times upper limit of normal were seen in 1.0% compared to 0.5% of patients in the linagliptin and glimepiride arms, respectively.

The clinical significance of elevations in lipase and amylase with linagliptin is unknown in the absence of potential signs and symptoms of pancreatitis [see Warnings and Precautions (5.2)].

Metformin

Decrease in Vitamin B12: In metformin clinical trials of 29-week duration, a decrease to subnormal levels of previously normal serum vitamin B12 levels was observed in approximately 7% of patients.

6.2 Postmarketing Experience

The following adverse reactions have been identified during postapproval use. Because these reactions are reported voluntarily from a population of uncertain size, it is generally not possible to reliably estimate their frequency or establish a causal relationship to drug exposure.

Linagliptin

- Gastrointestinal Disorders: Acute pancreatitis, including fatal pancreatitis [see Indications and Usage (1)], mouth ulceration, stomatitis
- Immune System Disorders: Hypersensitivity reactions including anaphylaxis, angioedema, and exfoliative skin conditions
- Musculoskeletal and Connective Tissue Disorders: Rhabdomyolysis, severe and disabling arthralgia
- Skin and Subcutaneous Tissue Disorders: Bullous pemphigoid, rash

Metformin

- Hepatobiliary Disorders: Cholestatic, hepatocellular, and mixed hepatocellular liver injury

7 DRUG INTERACTIONS

Table 2 describes clinically relevant interactions with JENTADUETO XR.

Table 2 Clinically Relevant Interactions with JENTADUETO XR
Carbonic Anhydrase Inhibitors
Clinical Impact | Topiramate or other carbonic anhydrase inhibitors (e.g., zonisamide, acetazolamide or dichlorphenamide) frequently cause a decrease in serum bicarbonate and induce non-anion gap, hyperchloremic metabolic acidosis. Concomitant use of these drugs with JENTADUETO XR may increase the risk of lactic acidosis.
Intervention | Consider more frequent monitoring of these patients.
Drugs that Reduce Metformin Clearance
Clinical Impact | Concomitant use of drugs that interfere with common renal tubular transport systems involved in the renal elimination of metformin (e.g., organic cationic transporter-2 [OCT2] / multidrug and toxin extrusion [MATE] inhibitors such as ranolazine, vandetanib, dolutegravir, and cimetidine) could increase systemic exposure to metformin and may increase the risk for lactic acidosis [see Clinical Pharmacology (12.3)].
Intervention | Consider the benefits and risks of concomitant use.
Alcohol
Clinical Impact | Alcohol is known to potentiate the effect of metformin on lactate metabolism.
Intervention | Warn patients against excessive alcohol intake while receiving JENTADUETO XR.
Insulin or Insulin Secretagogues
Clinical Impact | The risk of hypoglycemia is increased when JENTADUETO XR is used in combination with an insulin secretagogue (e.g., sulfonylurea) or insulin.
Intervention | Coadministration of JENTADUETO XR with an insulin secretagogue (e.g., sulfonylurea) or insulin may require lower dosages of the insulin secretagogue or insulin to reduce the risk of hypoglycemia.
Drugs Affecting Glycemic Control
Clinical Impact | Certain drugs tend to produce hyperglycemia and may lead to loss of glycemic control. These drugs include the thiazides and other diuretics, corticosteroids, phenothiazines, thyroid products, estrogens, oral contraceptives, phenytoin, nicotinic acid, sympathomimetics, calcium channel blocking drugs, and isoniazid.
Intervention | When such drugs are administered to a patient receiving JENTADUETO XR, the patient should be closely observed to maintain adequate glycemic control. When such drugs are withdrawn from a patient receiving JENTADUETO XR, the patient should be observed closely for hypoglycemia.
Inducers of P-glycoprotein or CYP3A4 Enzymes
Clinical Impact | Rifampin decreased linagliptin exposure, suggesting that the efficacy of linagliptin may be reduced when administered in combination with a strong P-gp or CYP3A4 inducer.
Intervention | Use of alternative treatments is strongly recommended when linagliptin is to be administered with a strong P-gp or CYP3A4 inducer.

8 USE IN SPECIFIC POPULATIONS

8.1 Pregnancy

Risk Summary

The limited data with JENTADUETO XR and linagliptin use in pregnant women are not sufficient to inform a JENTADUETO XR-associated or linagliptin-associated risk for major birth defects and miscarriage. Published studies with metformin use during pregnancy have not reported a clear association with metformin and major birth defect or miscarriage risk [see Data]. There are risks to the mother and fetus associated with poorly controlled diabetes in pregnancy [see Clinical Considerations].

In animal reproduction studies, no adverse developmental effects were observed when the combination of linagliptin and metformin was administered to pregnant rats during the period of organogenesis at doses similar to the maximum recommended clinical dose, based on exposure [see Data].

The estimated background risk of major birth defects is 6% to 10% in women with pre-gestational diabetes with a HbA1c>7 and has been reported to be as high as 20% to 25% in women with HbA1c>10. The estimated background risk of miscarriage for the indicated population is unknown. In the U.S. general population, the estimated background risk of major birth defects and miscarriage in clinically recognized pregnancies is 2% to 4% and 15% to 20%, respectively.

Clinical Considerations

Disease-associated maternal and/or embryo/fetal risk

Poorly controlled diabetes in pregnancy increases the maternal risk for diabetic ketoacidosis, preeclampsia, spontaneous abortions, preterm delivery, and delivery complications. Poorly controlled diabetes increases the fetal risk for major birth defects, stillbirth, and macrosomia related morbidity.

Data

Human Data

Published data from postmarketing studies have not reported a clear association with metformin and major birth defects, miscarriage, or adverse maternal or fetal outcomes when metformin was used during pregnancy. However, these studies cannot definitely establish the absence of any metformin-associated risk because of methodological limitations, including small sample size and inconsistent comparator groups.

Animal Data

Linagliptin and metformin, the components of JENTADUETO XR, were coadministered to pregnant Wistar Han rats during the period of organogenesis. No adverse developmental outcome was observed at doses similar to the maximum recommended clinical dose, based on exposure. At higher doses associated with maternal toxicity, the metformin component of the combination was associated with an increased incidence of fetal rib and scapula malformations at ≥9-times a 2,000 mg clinical dose, based on exposure.

Linagliptin

No adverse developmental outcome was observed when linagliptin was administered to pregnant Wistar Han rats and Himalayan rabbits during the period of organogenesis at doses up to 240 mg/kg/day and 150 mg/kg/day, respectively. These doses represent approximately 943-times (rats) and 1,943-times (rabbits) the 5 mg maximum clinical dose, based on exposure. No adverse functional, behavioral, or reproductive outcome was observed in offspring following administration of linagliptin to Wistar Han rats from gestation day 6 to lactation day 21 at a dose 49-times the maximum recommended human dose, based on exposure.

Linagliptin crosses the placenta into the fetus following oral dosing in pregnant rats and rabbits.

Metformin HCl

Metformin HCl did not cause adverse developmental effects when administered to pregnant Sprague Dawley rats and rabbits at doses up to 600 mg/kg/day during the period of organogenesis. This represents an exposure of approximately 2-and 6-times a clinical dose of 2,000 mg, based on body surface area (mg/m^2) for rats and rabbits, respectively.

8.2 Lactation

Risk Summary

There is limited information regarding the presence of JENTADUETO XR or its components (linagliptin or metformin) in human milk, the effects on the breastfed infant, or the effects on milk production. However, linagliptin is present in rat milk. Limited published studies report that metformin is present in human milk [see Data]. Therefore, the developmental and health benefits of breastfeeding should be considered along with the mother's clinical need for JENTADUETO XR and any potential adverse effects on the breastfed child from JENTADUETO XR or from the underlying maternal condition.

Data

Published clinical lactation studies report that metformin is present in human milk which resulted in infant doses approximately 0.11% to 1% of the maternal weight-adjusted dosage and a milk/plasma ratio ranging between 0.13 and 1. However, the studies were not designed to definitely establish the risk of use of metformin during lactation because of small sample size and limited adverse event data collected in infants.

8.3 Females and Males of Reproductive Potential

Discuss the potential for unintended pregnancy with premenopausal women as therapy with metformin may result in ovulation in some anovulatory women.

8.4 Pediatric Use

Safety and effectiveness of JENTADUETO XR have not been established in pediatric patients.

Effectiveness of linagliptin was not demonstrated in a 26-week randomized, double-blind, placebo-controlled trial (NCT03429543) in 157 pediatric patients aged 10 to 17 years with inadequately controlled type 2 diabetes mellitus.

8.5 Geriatric Use

Linagliptin is minimally excreted by the kidney; however, metformin is substantially excreted by the kidney [see Warnings and Precautions (5.1) and Clinical Pharmacology (12.3)].

Linagliptin

In linagliptin studies, 1,085 linagliptin-treated patients were 65 years of age and older and 131 patients were 75 years of age and older. In these linagliptin studies, no overall differences in safety or effectiveness of linagliptin were observed between geriatric patients and younger adult patients.

Metformin

Controlled clinical studies of metformin did not include sufficient numbers of elderly patients to determine whether they respond differently from younger patients. In general, dose selection for an elderly patient should be cautious, usually starting at the low end of the dosing range, reflecting the greater frequency of decreased hepatic, renal, or cardiac function, and of concomitant disease or other drug therapy and the higher risk of lactic acidosis. Assess renal function more frequently in elderly patients [see Contraindications (4), Warnings and Precautions (5.1), and Clinical Pharmacology (12.3)].

8.6 Renal Impairment

Metformin is substantially excreted by the kidney, and the risk of metformin accumulation and lactic acidosis increases with the degree of renal impairment.

JENTADUETO XR is contraindicated in severe renal impairment, patients with an estimated glomerular filtration rate (eGFR) below 30 mL/min/1.73 m^2 [see Dosage and Administration (2.2), Contraindications (4), Warnings and Precautions (5.1) and Clinical Pharmacology (12.3)].

In the linagliptin treatment arm of the CARMELINA trial [see Clinical Studies (14.2)], 2,200 (63%) patients had renal impairment (eGFR <60 mL/min/1.73m^2). Approximately 20% of the population had eGFR ≥45 to <60 mL/min/1.73 m^2, 28% of the population had eGFR ≥30 to <45 mL/min/1.73 m^2 and 15% had eGFR <30 mL/min/1.73 m^2. The overall incidence of adverse reactions were generally similar between the linagliptin and placebo treatment arms.

8.7 Hepatic Impairment

Use of metformin in patients with hepatic impairment has been associated with some cases of lactic acidosis. JENTADUETO XR is not recommended in patients with hepatic impairment [see Warnings and Precautions (5.1)].

10 OVERDOSAGE

In the event of an overdose with JENTADUETO XR, consider contacting the Poison Help line (1-800-222-1222) or a medical toxicologist for additional overdosage management recommendations.

Overdose of metformin HCl has occurred, including ingestion of amounts greater than 50 grams. Lactic acidosis has been reported in approximately 32% of metformin overdose cases [see Warnings and Precautions (5.1)]. Metformin is dialyzable with a clearance of up to 170 mL/min under good hemodynamic conditions. Therefore, hemodialysis may be useful for removal of accumulated drug from patients in whom metformin overdosage is suspected.

Removal of linagliptin by hemodialysis or peritoneal dialysis is unlikely.

11 DESCRIPTION

JENTADUETO XR tablets for oral use contain: linagliptin and metformin HCl.

Linagliptin

Linagliptin is an inhibitor of the dipeptidyl peptidase-4 (DPP-4) enzyme.

The chemical name of linagliptin is 1H-Purine-2,6-dione, 8-[(3R)-3-amino-1-piperidinyl]-7-(2-butyn-1-yl)-3,7-dihydro-3-methyl-1-[(4-methyl-2-quinazolinyl)methyl]-

The molecular formula is C25H28N8O2 and the molecular weight is 472.54 g/mol. The structural formula is:

Linagliptin is a white to yellowish, not or only slightly hygroscopic solid substance. It is very slightly soluble in water (0.9 mg/mL). Linagliptin is soluble in methanol (ca. 60 mg/mL), sparingly soluble in ethanol (ca. 10 mg/mL), very slightly soluble in isopropanol (<1 mg/mL), and very slightly soluble in acetone (ca. 1 mg/mL).

Metformin HCl

Metformin HCl (N,N-dimethylimidodicarbonimidic diamide hydrochloride) is a biguanide. Metformin HCl is a white to off-white crystalline compound with a molecular formula of C4H11N5∙HCl and a molecular weight of 165.63 g/mol. Metformin HCl is freely soluble in water and is practically insoluble in acetone, ether, and chloroform. The pKa of metformin is 12.4. The pH of a 1% aqueous solution of metformin hydrochloride is 6.68. The structural formula is:

JENTADUETO XR consists of an extended-release metformin core tablet that is coated with the immediate-release drug substance linagliptin. JENTADUETO XR is available for oral administration as tablets containing:

- 5 mg linagliptin and 1,000 mg metformin HCl (equivalent to 779.86 mg of metformin)
- 2.5 mg linagliptin and 1,000 mg metformin HCl (equivalent to 779.86 mg of metformin)

Each coated tablet of JENTADUETO XR contains the following inactive ingredients: Tablet core: hypromellose, magnesium stearate, and polyethylene oxide. Coating: arginine, carnauba wax, ferric oxide yellow (2.5 mg/1,000 mg), ferrosoferric oxide, hydroxypropyl cellulose, hypromellose, isopropyl alcohol, polyethylene glycol, propylene glycol, talc, and titanium dioxide.

12 CLINICAL PHARMACOLOGY

12.1 Mechanism of Action

JENTADUETO XR

JENTADUETO XR contains: linagliptin, a dipeptidyl peptidase-4 (DPP-4) inhibitor, and metformin, a biguanide.

Linagliptin

Linagliptin is an inhibitor of DPP-4, an enzyme that degrades the incretin hormones glucagon-like peptide-1 (GLP-1) and glucose-dependent insulinotropic polypeptide (GIP). Thus, linagliptin increases the concentrations of active incretin hormones, stimulating the release of insulin in a glucose-dependent manner and decreasing the levels of glucagon in the circulation. Both incretin hormones are involved in the physiological regulation of glucose homeostasis. Incretin hormones are secreted at a low basal level throughout the day and levels rise immediately after meal intake. GLP-1 and GIP increase insulin biosynthesis and secretion from pancreatic beta cells in the presence of normal and elevated blood glucose levels. Furthermore, GLP-1 also reduces glucagon secretion from pancreatic alpha cells, resulting in a reduction in hepatic glucose output.

Metformin HCl

Metformin is an antihyperglycemic agent which improves glucose tolerance in patients with type 2 diabetes mellitus, lowering both basal and postprandial plasma glucose. Metformin decreases hepatic glucose production, decreases intestinal absorption of glucose, and improves insulin sensitivity by increasing peripheral glucose uptake and utilization. With metformin therapy, insulin secretion remains unchanged while fasting insulin levels and day-long plasma insulin response may decrease.

12.2 Pharmacodynamics

Linagliptin

Linagliptin binds to DPP-4 in a reversible manner and increases the concentrations of incretin hormones. Linagliptin glucose-dependently increases insulin secretion and lowers glucagon secretion, thus resulting in a better regulation of the glucose homeostasis. Linagliptin binds selectively to DPP-4 and selectively inhibits DPP-4, but not DPP-8 or DPP-9 activity in vitro at concentrations approximating therapeutic exposures.

Cardiac Electrophysiology

In a randomized, placebo-controlled, active-comparator, 4-way crossover study, 36 healthy subjects were administered a single oral dose of linagliptin 5 mg, linagliptin 100 mg (20 times the recommended dose), moxifloxacin, and placebo. No increase in QTc was observed with either the recommended dose of 5 mg or the 100-mg dose. At the 100-mg dose, peak linagliptin plasma concentrations were approximately 38-fold higher than the peak concentrations following a 5-mg dose.

12.3 Pharmacokinetics

JENTADUETO XR

Administration of JENTADUETO XR with a high-fat meal resulted in up to 7% to 22% decrease in overall exposure (AUC0-72) of linagliptin; this effect is not clinically relevant. For metformin extended-release, high-fat meals increased systemic exposure (AUC0-tz) by approximately 54% to 71% relative to fasting, while Cmax is increased up to 11%. Meals prolonged Tmax by approximately 3 hours.

Absorption

Linagliptin

The absolute bioavailability of linagliptin is approximately 30%. Following oral administration, plasma concentrations of linagliptin decline in at least a biphasic manner with a long terminal half-life (>100 hours), related to the saturable binding of linagliptin to DPP-4. However, the prolonged elimination does not contribute to the accumulation of the drug. The effective half-life for accumulation of linagliptin, as determined from oral administration of multiple doses of linagliptin 5 mg, is approximately 12 hours. After once-daily dosing, steady-state plasma concentrations of linagliptin 5 mg are reached by the third dose, and Cmax and AUC increased by a factor of 1.3 at steady-state compared with the first dose. Plasma AUC of linagliptin increased in a less than dose-proportional manner in the dose range of 1 to 10 mg. The pharmacokinetics of linagliptin is similar in healthy subjects and in patients with type 2 diabetes mellitus.

Metformin HCl

Following a single oral dose of 1,000 mg (2 × 500 mg tablets) metformin extended-release after a meal, the time to reach maximum plasma metformin concentration (Tmax) is achieved at approximately 7 to 8 hours. In both single- and multiple-dose studies in healthy subjects, once daily 1,000 mg (2 × 500 mg tablets) dosing provides equivalent systemic exposure, as measured by AUC, and up to 35% higher Cmax of metformin relative to the immediate-release given as 500 mg twice daily.

Single oral doses of metformin extended-release from 500 mg to 2,500 mg resulted in less than proportional increase in both AUC and Cmax. Low-fat and high-fat meals increased the systemic exposure (as measured by AUC) from metformin extended-release tablets by about 38% and 73%, respectively, relative to fasting. Both meals prolonged metformin Tmax by approximately 3 hours but Cmax was not affected.

Distribution

Linagliptin

The mean apparent volume of distribution at steady-state following a single intravenous dose of linagliptin 5 mg to healthy subjects is approximately 1,110 L, indicating that linagliptin extensively distributes to the tissues. Plasma protein binding of linagliptin is concentration-dependent decreasing from about 99% at 1 nmol/L to 75% to 89% at ≥30 nmol/L, reflecting saturation of binding to DPP-4 with increasing concentration of linagliptin. At high concentrations, where DPP-4 is fully saturated, 70% to 80% of linagliptin remains bound to plasma proteins and 20% to 30% is unbound in plasma. Plasma binding is not altered in patients with renal or hepatic impairment.

Metformin HCl

The apparent volume of distribution (V/F) of metformin following single oral doses of immediate-release metformin HCl tablets 850 mg averaged 654±358 L. Metformin is negligibly bound to plasma proteins. Metformin partitions into erythrocytes, most likely as a function of time.

Elimination

Linagliptin: Linagliptin has a terminal half-life of about 200 hours at steady-state, though the accumulation half-life is about 11 hours. Renal clearance at steady-state was approximately 70 mL/min.

Metformin HCl: Metformin has a plasma elimination half-life of approximately 6.2 hours. In blood, the elimination half-life is approximately 17.6 hours, suggesting that the erythrocyte mass may be a compartment of distribution.

Metabolism

Linagliptin: Following oral administration, the majority (about 90%) of linagliptin is excreted unchanged, indicating that metabolism represents a minor elimination pathway. A small fraction of absorbed linagliptin is metabolized to a pharmacologically inactive metabolite, which shows a steady-state exposure of 13.3% relative to linagliptin.

Metformin HCl: Intravenous single-dose studies in normal subjects demonstrate that metformin does not undergo hepatic metabolism (no metabolites have been identified in humans), nor biliary excretion.

Excretion

Linagliptin: Following administration of an oral [^14C] linagliptin dose to healthy subjects, approximately 85% of the administered radioactivity was eliminated via the enterohepatic system (80%) or urine (5%) within 4 days of dosing.

Metformin HCl: Following oral administration, approximately 90% of the absorbed drug is excreted via the renal route within the first 24 hours. Renal clearance is approximately 3.5 times greater than creatinine clearance, which indicates that tubular secretion is the major route of metformin elimination.

Specific Populations

Renal Impairment

JENTADUETO XR: Studies characterizing the pharmacokinetics of linagliptin and metformin after administration of JENTADUETO XR in renally impaired patients have not been performed.

Linagliptin: Under steady-state conditions, linagliptin exposure in patients with mild renal impairment was comparable to healthy subjects. In patients with moderate renal impairment under steady-state conditions, mean exposure of linagliptin increased (AUCτ,ss by 71% and Cmax by 46%) compared with healthy subjects. This increase was not associated with a prolonged accumulation half-life, terminal half-life, or an increased accumulation factor. Renal excretion of linagliptin was below 5% of the administered dose and was not affected by decreased renal function.

Patients with type 2 diabetes mellitus and severe renal impairment showed steady-state exposure approximately 40% higher than that of patients with type 2 diabetes mellitus and normal renal function (increase in AUC by 42% and Cmax by 35%). For both type 2 diabetes mellitus groups, renal excretion was below 7% of the administered dose.

These findings were further supported by the results of population pharmacokinetic analyses.

Metformin HCl: In patients with decreased renal function, the plasma and blood half-life of metformin is prolonged and the renal clearance is decreased [see Contraindications (4) and Warnings and Precautions (5.1)].

Hepatic Impairment

JENTADUETO XR: Studies characterizing the pharmacokinetics of linagliptin and metformin after administration of JENTADUETO XR in hepatically impaired patients have not been performed [see Warnings and Precautions (5.1)].

Linagliptin: In patients with mild hepatic impairment (Child-Pugh class A) steady-state exposure (AUCτ,ss) of linagliptin was approximately 25% lower and Cmax,ss was approximately 36% lower than in healthy subjects. In patients with moderate hepatic impairment (Child-Pugh class B), AUCss of linagliptin was about 14% lower and Cmax,ss was approximately 8% lower than in healthy subjects. Patients with severe hepatic impairment (Child-Pugh class C) had comparable exposure of linagliptin in terms of AUC0-24 and approximately 23% lower Cmax compared with healthy subjects. Reductions in the pharmacokinetic parameters seen in patients with hepatic impairment did not result in reductions in DPP-4 inhibition.

Metformin HCl: No pharmacokinetic studies of metformin have been conducted in patients with hepatic impairment.

Effects of Age, Body Mass Index (BMI), Gender, and Race

Linagliptin: Based on the population pharmacokinetic analysis, age, BMI, gender, and race do not have a clinically meaningful effect on pharmacokinetics of linagliptin [see Use in Specific Populations (8.5)].

Metformin HCl: Metformin pharmacokinetic parameters did not differ significantly between normal subjects and patients with type 2 diabetes mellitus when analyzed according to gender. Similarly, in controlled clinical studies in patients with type 2 diabetes mellitus, the antihyperglycemic effect of metformin was comparable in males and females.

Limited data from controlled pharmacokinetic studies of metformin in healthy elderly subjects suggest that total plasma clearance of metformin is decreased, the half-life is prolonged, and Cmax is increased, compared with healthy young subjects. From these data, it appears that the change in metformin pharmacokinetics with aging is primarily accounted for by a change in renal function.

No studies of metformin pharmacokinetic parameters according to race have been performed. In controlled clinical studies of metformin HCl in patients with type 2 diabetes mellitus, the antihyperglycemic effect was comparable in Caucasians (n=249), Blacks (n=51), and Hispanics (n=24).

Drug Interactions

Pharmacokinetic drug interaction studies with JENTADUETO XR have not been performed; however, such studies have been conducted with the individual components of JENTADUETO XR (linagliptin and metformin HCl).

Linagliptin

In vitro Assessment of Drug Interactions

Linagliptin is a weak to moderate inhibitor of CYP isozyme CYP3A4, but does not inhibit other CYP isozymes and is not an inducer of CYP isozymes, including CYP1A2, 2A6, 2B6, 2C8, 2C9, 2C19, 2D6, 2E1, and 4A11.

Linagliptin is a P-glycoprotein (P-gp) substrate, and inhibits P-gp mediated transport of digoxin at high concentrations. Based on these results and in vivo drug interaction studies, linagliptin is considered unlikely to cause interactions with other P-gp substrates at therapeutic concentrations.

In vivo Assessment of Drug Interactions

Strong inducers of CYP3A4 or P-gp (e.g., rifampin) decrease exposure to linagliptin to subtherapeutic and likely ineffective concentrations [see Drug Interactions (7)]. In vivo studies indicated evidence of a low propensity for causing drug interactions with substrates of CYP3A4, CYP2C9, CYP2C8, P-gp, and organic cationic transporter (OCT).

Table 3 describes the effect of coadministered drugs on systemic exposure of linagliptin.

Table 3 Effect of Coadministered Drugs on Systemic Exposure of Linagliptin
Coadministered Drug | Dosing of Coadministered Drug* | Dosing of Linagliptin* | Geometric Mean Ratio (ratio with/without coadministered drug) No effect=1.0
 |  |  | AUC† | Cmax
Metformin | 850 mg TID | 10 mg QD | 1.20 | 1.03
Glyburide | 1.75 mg# | 5 mg QD | 1.02 | 1.01
Pioglitazone | 45 mg QD | 10 mg QD | 1.13 | 1.07
Ritonavir | 200 mg BID | 5 mg# | 2.01 | 2.96
Rifampin** | 600 mg QD | 5 mg QD | 0.60 | 0.56
*Multiple dose (steady-state) unless otherwise noted
**For information regarding clinical recommendations [see Drug Interactions (7)].
# Single dose
†AUC=AUC(0 to 24 hours) for single-dose treatments and AUC = AUC(TAU) for multiple-dose treatments
QD=once daily
BID=twice daily
TID=three times daily

Table 4 describes the effect of linagliptin on systemic exposure of coadministered drugs.

Table 4 Effect of Linagliptin on Systemic Exposure of Coadministered Drugs
Coadministered Drug | Dosing of Coadministered Drug* | Dosing of Linagliptin* | Geometric Mean Ratio (ratio with/without coadministered drug) No effect=1.0
 |  |  |  | AUC† | Cmax
Metformin | 850 mg TID | 10 mg QD | metformin | 1.01 | 0.89
Glyburide | 1.75 mg# | 5 mg QD | glyburide | 0.86 | 0.86
Pioglitazone | 45 mg QD | 10 mg QD | pioglitazone | 0.94 | 0.86
Pioglitazone | 45 mg QD | 10 mg QD | metabolite M-III | 0.98 | 0.96
Pioglitazone | 45 mg QD | 10 mg QD | metabolite M-IV | 1.04 | 1.05
Digoxin | 0.25 mg QD | 5 mg QD | digoxin | 1.02 | 0.94
Simvastatin | 40 mg QD | 10 mg QD | simvastatin | 1.34 | 1.10
Simvastatin | 40 mg QD | 10 mg QD | simvastatin acid | 1.33 | 1.21
Warfarin | 10 mg# | 5 mg QD | R-warfarin | 0.99 | 1.00
Warfarin | 10 mg# | 5 mg QD | S-warfarin | 1.03 | 1.01
Warfarin | 10 mg# | 5 mg QD | INR | 0.93** | 1.04**
Warfarin | 10 mg# | 5 mg QD | PT | 1.03** | 1.15**
Ethinylestradiol and levonorgestrel | ethinylestradiol 0.03 mg and levonorgestrel 0.150 mg QD | 5 mg QD | ethinylestradiol | 1.01 | 1.08
Ethinylestradiol and levonorgestrel | ethinylestradiol 0.03 mg and levonorgestrel 0.150 mg QD | 5 mg QD | levonorgestrel | 1.09 | 1.13
* Multiple dose (steady-state) unless otherwise noted
# Single dose
†AUC=AUC(INF) for single-dose treatments and AUC = AUC(TAU) for multiple-dose treatments
**AUC=AUC(0-168) and Cmax=Emax for pharmacodynamic end points
INR = International Normalized Ratio
PT=Prothrombin Time
QD=once daily
TID=three times daily

Metformin HCl

Table 5 describes the effect of coadministered drugs on plasma metformin systemic exposure.

Table 5 Effect of Coadministered Drugs on Plasma Metformin Systemic Exposure
Coadministered Drug | Dosing of Coadministered Drug* | Dosing of Metformin* | Geometric Mean Ratio (ratio with/without coadministered drug) No effect=1.0
 |  |  |  | AUC† | Cmax
Glyburide | 5 mg | 500 mg ≠ | metformin | 0.98‡ | 0.99‡
Furosemide | 40 mg | 850 mg | metformin | 1.09‡ | 1.22‡
Nifedipine | 10 mg | 850 mg | metformin | 1.16 | 1.21
Propranolol | 40 mg | 850 mg | metformin | 0.90 | 0.94
Ibuprofen | 400 mg | 850 mg | metformin | 1.05‡ | 1.07‡
Cationic drugs eliminated by renal tubular secretion may reduce metformin elimination [see Drug Interactions (7)].
Cimetidine | 400 mg | 850 mg | metformin | 1.40 | 1.61
Carbonic anhydrase inhibitors may cause metabolic acidosis [see Drug Interactions (7)].
Topiramate** | 100 mg | 500 mg | metformin | 1.25 | 1.17
*All metformin and coadministered drugs were given as single doses
† AUC=AUC(INF)
≠metformin HCl extended-release tablets 500 mg
‡Ratio of arithmetic means
**At steady-state with topiramate 100 mg every 12 hours and metformin 500 mg every 12 hours; AUC = AUC(0-12 hours)

Table 6 describes the effect of metformin on coadministered drug systemic exposure.

Table 6 Effect of Metformin on Coadministered Drug Systemic Exposure
Coadministered Drug | Dosing of Coadministered Drug* | Dosing of Metformin* | Geometric Mean Ratio (ratio with/without metformin) No effect=1.0
 |  |  |  | AUC† | Cmax
Glyburide | 5 mg | 500 mg§ | glyburide | 0.78‡ | 0.63‡
Furosemide | 40 mg | 850 mg | furosemide | 0.87‡ | 0.69‡
Nifedipine | 10 mg | 850 mg | nifedipine | 1.10§ | 1.08
Propranolol | 40 mg | 850 mg | propranolol | 1.01§ | 0.94
Ibuprofen | 400 mg | 850 mg | ibuprofen | 0.97¶ | 1.01¶
Cimetidine | 400 mg | 850 mg | cimetidine | 0.95§ | 1.01
*All metformin and coadministered drugs were given as single doses
†AUC=AUC(INF) unless otherwise noted
‡Ratio of arithmetic means, p-value of difference <0.05
§AUC(0-24 hours) reported
¶Ratio of arithmetic means

13 NONCLINICAL TOXICOLOGY

13.1 Carcinogenesis, Mutagenesis, Impairment of Fertility

JENTADUETO XR

No carcinogenicity, mutagenicity, or impairment of fertility studies have been conducted with the combination of linagliptin and metformin HCl.

Linagliptin

Linagliptin did not increase the incidence of tumors in male and female rats in a 2-year study at doses of 6, 18, and 60 mg/kg. The highest dose of 60 mg/kg is approximately 418 times the clinical dose of 5 mg/day based on AUC exposure. Linagliptin did not increase the incidence of tumors in mice in a 2-year study at doses up to 80 mg/kg (males) and 25 mg/kg (females), or approximately 35 and 270 times the clinical dose based on AUC exposure. Higher doses of linagliptin in female mice (80 mg/kg) increased the incidence of lymphoma at approximately 215 times the clinical dose based on AUC exposure.

Linagliptin was not mutagenic or clastogenic with or without metabolic activation in the Ames bacterial mutagenicity assay, a chromosomal aberration test in human lymphocytes, and an in vivo micronucleus assay.

In fertility studies in rats, linagliptin had no adverse effects on early embryonic development, mating, fertility, or bearing live young up to the highest dose of 240 mg/kg (approximately 943 times the clinical dose based on AUC exposure).

Metformin HCl

Long-term carcinogenicity studies have been performed in Sprague Dawley rats at doses of 150, 300, and 450 mg/kg/day in males and 150, 450, 900, and 1,200 mg/kg/day in females. These doses are approximately 2, 4, and 8 times in males, and 3, 7, 12, and 16 times in females of the maximum recommended human daily dose of 2,000 mg/kg/day based on body surface area comparisons. No evidence of carcinogenicity with metformin was found in either male or female rats. A carcinogenicity study was also performed in Tg.AC transgenic mice at doses of up to 2,000 mg/kg/day applied dermally. No evidence of carcinogenicity was observed in male or female mice.

Genotoxicity assessments in the Ames test, gene mutation test (mouse lymphoma cells), chromosomal aberrations test (human lymphocytes) and in vivo mouse micronucleus tests were negative.

Fertility of male or female rats was unaffected by metformin when administered at doses as high as 600 mg/kg/day, which is approximately 2 times the MRHD based on body surface area comparisons.

14 CLINICAL STUDIES

14.1 Glycemic Control Trials in Adults with Type 2 Diabetes Mellitus

Initial Combination Therapy with Linagliptin and Metformin

A total of 791 patients with type 2 diabetes mellitus and inadequate glycemic control on diet and exercise participated in the 24-week, randomized, double-blind, portion of this placebo-controlled factorial trial designed to assess the efficacy of linagliptin as initial therapy with metformin. Patients on an antihyperglycemic agent (52%) underwent a drug washout period of 4 weeks' duration. After the washout period and after completing a 2-week single-blind placebo run-in period, patients with inadequate glycemic control (A1C ≥7.0% to ≤10.5%) were randomized. Patients with inadequate glycemic control (A1C ≥7.5% to <11.0%) not on antihyperglycemic agents at trial entry (48%) immediately entered the 2-week single-blind placebo run-in period and then were randomized. Randomization was stratified by baseline A1C (<8.5% vs ≥8.5%) and use of a prior oral antidiabetic drug (none vs monotherapy). Patients were randomized in a 1:2:2:2:2:2 ratio to either placebo or one of 5 active-treatment arms. Approximately equal numbers of patients were randomized to receive initial therapy with 5 mg of linagliptin once daily, 500 mg or 1,000 mg of metformin twice daily, or 2.5 mg of linagliptin twice daily in combination with 500 mg or 1,000 mg of metformin twice daily. Patients who failed to meet specific glycemic goals during the trial were treated with sulfonylurea, thiazolidinedione, or insulin rescue therapy.

Initial therapy with the combination of linagliptin and metformin provided significant improvements in A1C, and fasting plasma glucose (FPG) compared to placebo, to metformin alone, and to linagliptin alone (Table 7, Figure 1). The adjusted mean treatment difference in A1C from baseline to week 24 (LOCF) was -0.5% (95% CI -0.7, -0.3; p<0.0001) for linagliptin 2.5 mg/metformin 1,000 mg twice daily compared to metformin 1,000 mg twice daily; -1.1% (95% CI -1.4, -0.9; p<0.0001) for linagliptin 2.5 mg/metformin 1,000 mg twice daily compared to linagliptin 5 mg once daily; -0.6% (95% CI -0.8, -0.4; p<0.0001) for linagliptin 2.5 mg/metformin 500 mg twice daily compared to metformin 500 mg twice daily; and -0.8% (95% CI -1.0, -0.6; p<0.0001) for linagliptin 2.5 mg/metformin 500 mg twice daily compared to linagliptin 5 mg once daily.

Lipid effects were generally neutral. No meaningful change in body weight was noted in any of the 6 treatment groups.

Table 7 Glycemic Parameters at Final Visit (24-Week Trial) for Linagliptin and Metformin, Alone and in Combination in Randomized Patients with Type 2 Diabetes Mellitus Inadequately Controlled on Diet and Exercise**
 | Placebo | Linagliptin 5 mg Once Daily* | Metformin 500 mg Twice Daily | Linagliptin 2.5 mg Twice Daily* + Metformin 500 mg Twice Daily | Metformin 1,000 mg Twice Daily | Linagliptin 2.5 mg Twice Daily* + Metformin 1,000 mg Twice Daily
A1C (%)
Number of patients | n=65 | n=135 | n=141 | n=137 | n=138 | n=140
Baseline (mean) | 8.7 | 8.7 | 8.7 | 8.7 | 8.5 | 8.7
Change from baseline (adjusted mean****) | 0.1 | -0.5 | -0.6 | -1.2 | -1.1 | -1.6
Difference from placebo (adjusted mean) (95% CI) | -- | -0.6 (-0.9, -0.3) | -0.8 (-1.0, -0.5) | -1.3 (-1.6, -1.1) | -1.2 (-1.5, -0.9) | -1.7 (-2.0, -1.4)
Patients [n (%)] achieving A1C <7%*** | 7 (10.8) | 14 (10.4) | 26 (18.6) | 41 (30.1) | 42 (30.7) | 74 (53.6)
Patients (%) receiving rescue medication | 29.2 | 11.1 | 13.5 | 7.3 | 8.0 | 4.3
FPG (mg/dL)
Number of patients | n=61 | n=134 | n=136 | n=135 | n=132 | n=136
Baseline (mean) | 203 | 195 | 191 | 199 | 191 | 196
Change from baseline (adjusted mean****) | 10 | -9 | -16 | -33 | -32 | -49
Difference from placebo (adjusted mean) (95% CI) | -- | -19 (-31, -6) | -26 (-38, -14) | -43 (-56, -31) | -42 (-55, -30) | -60 (-72, -47)
*Total daily dosage of linagliptin is equal to 5 mg
**Full analysis population using last observation on trial
***Metformin 500 mg twice daily, n=140; Linagliptin 2.5 mg twice daily + Metformin 500 mg twice daily, n=136; Metformin 1,000 mg twice daily, n=137; Linagliptin 2.5 mg twice daily + Metformin 1,000 mg twice daily, n=138
****HbA1c: ANCOVA model included treatment and number of prior OADs as class-effects, as well as baseline HbA1c as continuous covariates. FPG: ANCOVA model included treatment and number of prior OADs as class-effects, as well as baseline HbA1c and baseline FPG as continuous covariates.

Figure 1 Adjusted Mean Change from Baseline for A1C (%) over 24 Weeks with Linagliptin and Metformin, Alone and in Combination in Patients with Type 2 Diabetes Mellitus Inadequately Controlled with Diet and Exercise - FAS completers.

Initial Combination Therapy with Linagliptin and Metformin vs Linagliptin in Treatment-Naïve Patients

A total of 316 patients with type 2 diabetes mellitus diagnosed within the previous 12 months and treatment-naïve (no antidiabetic therapy for 12 weeks prior to randomization) and inadequate glycemic control (A1C ≥8.5% to ≤12.0%) participated in a 24-week, randomized, double-blind, trial designed to assess the efficacy of linagliptin in combination with metformin vs linagliptin. Patients were randomized (1:1), after a 2-week run-in period, to either linagliptin 5 mg plus metformin (1,500 to 2,000 mg per day, n=159) or linagliptin 5 mg plus placebo, (n=157) administered once daily. Patients in the linagliptin and metformin treatment group were up-titrated to a maximum tolerated dosage of metformin (1,000 to 2,000 mg per day) over a three-week period.

Initial therapy with the combination of linagliptin and metformin provided statistically significant improvements in A1C compared to linagliptin (Table 8). The mean difference between groups in A1C change from baseline was -0.8% with 2-sided 95% confidence interval (-1.23%, -0.45%).

Table 8 Glycemic Parameters at 24 Weeks in Trial Comparing Linagliptin in Combination with Metformin to Linagliptin in Treatment-Naïve Patients*
 | Linagliptin 5 mg + Metformin | Linagliptin 5 mg + Placebo
A1C (%)*
Number of patients | n=153 | n=150
Baseline (mean) | 9.8 | 9.9
Change from baseline (adjusted mean) | -2.9 | -2
Difference from linagliptin (adjusted mean**) (95% CI) | -0.84† (-1.23, -0.45) | --
Patients [n (%)] achieving A1C <7%* | 82 (53.6) | 45 (30)
FPG (mg/dL)*
Number of patients | n=153 | n=150
Baseline (mean) | 196 | 198
Change from baseline (adjusted mean) | -54 | -35
Difference from linagliptin (adjusted mean**) (95% CI) | -18†† (-31, -5.5) | --
†p<0.0001 compared to linagliptin, ††p=0.0054 compared to linagliptin
*Full analysis set population
**A1C: MMRM model included treatment, continuous baseline A1C, baseline A1C by visit interaction, visit by treatment interaction, baseline renal impairment by treatment interaction and baseline renal impairment by treatment by visit interaction. FPG: MMRM model included treatment, continuous baseline A1C, continuous baseline FPG, baseline FPG by visit interaction, visit by treatment interaction, baseline renal impairment by treatment interaction and baseline renal impairment by treatment by visit interaction.

The adjusted mean changes for A1C (%) from baseline over time for linagliptin and metformin as compared to linagliptin alone were maintained throughout the 24-week treatment period. Using the completers analysis the respective adjusted means for A1C (%) changes from baseline for linagliptin and metformin as compared to linagliptin alone were -1.9 and -1.3 at week 6, -2.6 and -1.8 at week 12, -2.7 and -1.9 at week 18, and -2.7 and -1.9 at week 24.

Changes in body weight from baseline were not clinically significant in either treatment group.

Add-On Combination Therapy with Metformin

A total of 701 patients with type 2 diabetes mellitus participated in a 24-week, randomized, double-blind, placebo-controlled trial designed to assess the efficacy of linagliptin in combination with metformin. Patients already on metformin (n=491) at a dosage of at least 1,500 mg per day were randomized after completing a 2-week, open-label, placebo run-in period. Patients on metformin and another antihyperglycemic agent (n=207) were randomized after a run-in period of approximately 6 weeks on metformin (at a dosage of at least 1,500 mg per day) in monotherapy. Patients were randomized to the addition of either linagliptin 5 mg or placebo, administered once daily. Patients who failed to meet specific glycemic goals during the studies were treated with glimepiride rescue.

In combination with metformin, linagliptin provided statistically significant improvements in A1C, FPG, and 2-hour PPG compared with placebo (Table 9). Rescue glycemic therapy was used in 7.8% of patients treated with linagliptin 5 mg and in 18.9% of patients treated with placebo. A similar decrease in body weight was observed for both treatment groups.

Table 9 Glycemic Parameters in Placebo-Controlled Trial for Linagliptin in Combination with Metformin*
 | Linagliptin 5 mg + Metformin | Placebo + Metformin
A1C (%)
Number of patients | n=513 | n=175
Baseline (mean) | 8.1 | 8.0
Change from baseline (adjusted mean***) | -0.5 | 0.15
Difference from placebo + metformin (adjusted mean) (95% CI) | -0.6 (-0.8, -0.5) | --
Patients [n (%)] achieving A1C <7%** | 127 (26.2) | 15 (9.2)
FPG (mg/dL)
Number of patients | n=495 | n=159
Baseline (mean) | 169 | 164
Change from baseline (adjusted mean***) | -11 | 11
Difference from placebo + metformin (adjusted mean) (95% CI) | -21 (-27, -15) | --
2-hour PPG (mg/dL)
Number of patients | n=78 | n=21
Baseline (mean) | 270 | 274
Change from baseline (adjusted mean***) | -49 | 18
Difference from placebo + metformin (adjusted mean) (95% CI) | -67 (-95, -40) | --
* Full analysis population using last observation on trial
**Linagliptin 5 mg + Metformin, n=485; Placebo + Metformin, n=163
***HbA1c: ANCOVA model included treatment and number of prior oral OADs as class-effects, as well as baseline HbA1c as continuous covariates. FPG: ANCOVA model included treatment and number of prior OADs as class-effects, as well as baseline HbA1c and baseline FPG as continuous covariates. PPG: ANCOVA model included treatment and number of prior OADs as class-effects, as well as baseline HbA1c and baseline postprandial glucose after two hours as covariate.

Active-Controlled Trial vs Glimepiride in Combination with Metformin

The efficacy of linagliptin was evaluated in a 104-week double-blind, glimepiride-controlled non-inferiority trial in type 2 diabetic patients with insufficient glycemic control despite metformin therapy. Patients being treated with metformin only entered a run-in period of 2 weeks' duration, whereas patients pretreated with metformin and one additional antihyperglycemic agent entered a run-in treatment period of 6 weeks' duration with metformin monotherapy (dosage of ≥1,500 mg per day) and washout of the other agent. After an additional 2-week placebo run-in period, those with inadequate glycemic control (A1C 6.5% to 10%) were randomized 1:1 to the addition of linagliptin 5 mg once daily or glimepiride. Randomization was stratified by baseline HbA1c (<8.5% vs ≥8.5%), and the previous use of antidiabetic drugs (metformin alone vs metformin plus one other OAD). Patients receiving glimepiride were given an initial dosage of 1 mg/day and then electively titrated over the next 12 weeks to a maximum dosage of 4 mg/day as needed to optimize glycemic control. Thereafter, the glimepiride dosage was to be kept constant, except for down-titration to prevent hypoglycemia.

After 52 weeks and 104 weeks, linagliptin and glimepiride both had reductions from baseline in A1C (52 weeks: -0.4% for linagliptin, -0.6% for glimepiride; 104 weeks: -0.2% for linagliptin, -0.4% for glimepiride) from a baseline mean of 7.7% (Table 10). The mean difference between groups in A1C change from baseline was 0.2% with 2-sided 97.5% confidence interval (0.1%, 0.3%) for the intent-to-treat population using last observation carried forward. These results were consistent with the completers analysis.

Table 10 Glycemic Parameters at 52 and 104 Weeks in Trial Comparing Linagliptin to Glimepiride as Add-On Therapy in Patients Inadequately Controlled on Metformin**
 | Week 52 |  | Week 104
 | Linagliptin 5 mg + Metformin | Glimepiride + Metformin (mean glimepiride dosage 3 mg) | Linagliptin 5 mg + Metformin | Glimepiride + Metformin (mean glimepiride dosage 3 mg)
A1C (%)
Number of patients | n=764 | n=755 | n=764 | n=755
Baseline (mean) | 7.7 | 7.7 | 7.7 | 7.7
Change from baseline (adjusted mean***) | -0.4 | -0.6 | -0.2 | -0.4
Difference from glimepiride (adjusted mean) (97.5% CI) | 0.2 (0.1, 0.3) | -- | 0.2 (0.1, 0.3) | --
FPG (mg/dL)
Number of patients | n=733 | n=725 | n=733 | n=725
Baseline (mean) | 164 | 166 | 164 | 166
Change from baseline (adjusted mean***) | -8* | -15 | -2† | -9
*p<0.0001 vs glimepiride; †p=0.0012 vs glimepiride
**Full analysis population using last observation on trial
***HbA1c: ANCOVA model included treatment and number of prior OADs as class-effects, as well as baseline HbA1c as continuous covariates. FPG: ANCOVA model included treatment and number of prior OADs as class-effects, as well as baseline HbA1c and baseline FPG as continuous covariates.

Patients treated with linagliptin had a mean baseline body weight of 86 kg and were observed to have an adjusted mean decrease in body weight of 1.1 kg at 52 weeks and 1.4 kg at 104 weeks. Patients on glimepiride had a mean baseline body weight of 87 kg and were observed to have an adjusted mean increase from baseline in body weight of 1.4 kg at 52 weeks and 1.3 kg at 104 weeks (treatment difference p<0.0001 for both timepoints).

Add-On Combination Therapy with Metformin and a Sulfonylurea

A total of 1,058 patients with type 2 diabetes mellitus participated in a 24-week, randomized, double-blind, placebo-controlled trial designed to assess the efficacy of linagliptin in combination with a sulfonylurea and metformin. The most common sulfonylureas used by patients in the trial were glimepiride (31%), glibenclamide (26%), and gliclazide (26% [not available in the United States]). Patients on a sulfonylurea and metformin were randomized to receive linagliptin 5 mg or placebo, each administered once daily. Patients who failed to meet specific glycemic goals during the trial were treated with pioglitazone rescue. Glycemic end points measured included A1C and FPG.

In combination with a sulfonylurea and metformin, linagliptin provided statistically significant improvements in A1C and FPG compared with placebo (Table 11). In the entire trial population (patients on linagliptin in combination with a sulfonylurea and metformin), a mean reduction from baseline relative to placebo in A1C of -0.6% and in FPG of -13 mg/dL was seen. Rescue therapy was used in 5.4% of patients treated with linagliptin 5 mg and in 13% of patients treated with placebo. Change from baseline in body weight did not differ significantly between the groups.

Table 11 Glycemic Parameters at Final Visit (24-Week Trial) for Linagliptin in Combination with Metformin and Sulfonylurea*
 | Linagliptin 5 mg + Metformin + SU | Placebo + Metformin + SU
A1C (%)
Number of patients | n=778 | n=262
Baseline (mean) | 8.2 | 8.1
Change from baseline (adjusted mean***) | -0.7 | -0.1
Difference from placebo (adjusted mean) (95% CI) | -0.6 (-0.7, -0.5) | --
Patients [n (%)] achieving A1C <7%** | 217 (29.2) | 20 (8.1)
FPG (mg/dL)
Number of patients | n=739 | n=248
Baseline (mean) | 159 | 163
Change from baseline (adjusted mean***) | -5 | 8
Difference from placebo (adjusted mean) (95% CI) | -13 (-18, -7) | --
SU=sulfonylurea
*Full analysis population using last observation on trial
**Linagliptin 5 mg + Metformin + SU, n=742; Placebo + Metformin + SU, n=247
***HbA1c: ANCOVA model included treatment as class-effects and baseline HbA1c as continuous covariates. FPG: ANCOVA model included treatment as class-effects, as well as baseline HbA1c and baseline FPG as continuous covariates.

14.2 Linagliptin Cardiovascular Safety Trials in Patients with Type 2 Diabetes Mellitus

CARMELINA

The cardiovascular risk of linagliptin was evaluated in CARMELINA, a multi-national, multi-center, placebo-controlled, double-blind, parallel group trial comparing linagliptin (N=3,494) to placebo (N=3,485) in adult patients with type 2 diabetes mellitus and a history of established macrovascular and/or renal disease. The trial compared the risk of major adverse cardiovascular events (MACE) between linagliptin and placebo when these were added to standard of care treatments for diabetes mellitus and other cardiovascular risk factors. The trial was event driven, the median duration of follow-up was 2.2 years and vital status was obtained for 99.7% of patients.

Patients were eligible to enter the trial if they were adults with type 2 diabetes mellitus, with HbA1c of 6.5% to 10%, and had either albuminuria and previous macrovascular disease (39% of enrolled population), or evidence of impaired renal function by eGFR and Urinary Albumin Creatinine Ratio (UACR) criteria (42% of enrolled population), or both (18% of enrolled population).

At baseline the mean age was 66 years and the population was 63% male, 80% White, 9% Asian, 6% Black or African American and 36% were of Hispanic or Latino ethnicity. Mean HbA1c was 8.0% and mean duration of type 2 diabetes mellitus was 15 years. The trial population included 17% patients ≥75 years of age and 62% patients with renal impairment defined as eGFR <60 mL/min/1.73 m^2. The mean eGFR was 55 mL/min/1.73 m^2 and 27% of patients had mild renal impairment (eGFR 60 to 90 mL/min/1.73 m^2), 47% of patients had moderate renal impairment (eGFR 30 to <60 mL/min/1.73 m^2) and 15% of patients had severe renal impairment (eGFR <30 mL/min/1.73 m^2). Patients were taking at least one antidiabetic drug (97%), and the most common were insulin and analogues (57%), metformin (54%) and sulfonylurea (32%). Patients were also taking antihypertensives (96%), lipid lowering drugs (76%) with 72% on statin, and aspirin (62%).

The primary endpoint, MACE, was the time to first occurrence of one of three composite outcomes which included cardiovascular death, non-fatal myocardial infarction or non-fatal stroke. The trial was designed as a non-inferiority trial with a pre-specified risk margin of 1.3 for the hazard ratio of MACE.

The results of CARMELINA, including the contribution of each component to the primary composite endpoint, are shown in Table 12. The estimated hazard ratio for MACE associated with linagliptin relative to placebo was 1.02 with a 95% confidence interval of (0.89, 1.17). The upper bound of this confidence interval, 1.17, excluded the risk margin of 1.3. The Kaplan-Meier curve depicting time to first occurrence of MACE is shown in Figure 2.

Table 12 Major Adverse Cardiovascular Events (MACE) by Treatment Group in the CARMELINA Trial
 | Linagliptin 5 mg n = 3,494 |  | Placebo n = 3,485 |  | Hazard Ratio
 | Number of Subjects (%) | Incidence Rate per 1,000 PY* | Number of Subjects (%) | Incidence Rate per 1,000 PY* | (95% CI)
Composite of first event of CV death, non-fatal myocardial infarction (MI), or non-fatal stroke (MACE) | 434 (12.4) | 57.7 | 420 (12.1) | 56.3 | 1.02 (0.89, 1.17)
CV death** | 255 (7.3) | 32.6 | 264 (7.6) | 34.0 | 0.96 (0.81, 1.14)
Non-fatal MI** | 156 (4.5) | 20.6 | 135 (3.9) | 18.0 | 1.15 (0.91, 1.45)
Non-fatal stroke** | 65 (1.9) | 8.5 | 73 (2.1) | 9.6 | 0.88 (0.63, 1.23)
*PY=patient years
**A patient may have experienced more than one component; therefore, the sum of the components is larger than the number of patients who experienced the composite outcome.

Figure 2 Kaplan-Meier: Time to First Occurrence of MACE in the CARMELINA Trial

CAROLINA

The cardiovascular risk of linagliptin was evaluated in CAROLINA, a multi-center, multi-national, randomized, double-blind parallel group trial comparing linagliptin (N=3,023) to glimepiride (N=3,010) in adult patients with type 2 diabetes mellitus and a history of established cardiovascular disease and/or multiple cardiovascular risk factors. The trial compared the risk of major adverse cardiovascular events (MACE) between linagliptin and glimepiride when these were added to standard of care treatments for diabetes mellitus and other cardiovascular risk factors. The trial was event driven, the median duration of follow-up was 6.23 years and vital status was obtained for 99.3% of patients.

Patients were eligible to enter the trial if they were adults with type 2 diabetes mellitus with insufficient glycemic control (defined as HbA1c of 6.5% to 8.5% or 6.5% to 7.5% depending on whether treatment-naïve, on monotherapy or on combination therapy), and were defined to be at high cardiovascular risk with previous vascular disease, evidence of vascular related end-organ damage, age ≥70 years, and/or two cardiovascular risk factors (duration of diabetes mellitus >10 years, systolic blood pressure >140 mmHg, current smoker, LDL cholesterol ≥135 mg/dL).

At baseline, the mean age was 64 years and the population was 60% male, 73% White, 18% Asian, 5% Black or African American, and 17% were of Hispanic or Latino ethnicity. The mean HbA1c was 7.15% and mean duration of type 2 diabetes was 7.6 years. The trial population included 34% patients ≥70 years of age and 19% patients with renal impairment defined as eGFR <60 mL/min/1.73m^2. The mean eGFR was 77 mL/min/1.73m^2. Patients were taking at least one antidiabetic drug (91%) and the most common were metformin (83%) and sulfonylurea (28%). Patients were also taking antihypertensives (89%), lipid lowering drugs (70%) with 65% on statin, and aspirin (47%).

The primary endpoint, MACE, was the time to first occurrence of one of three composite outcomes which included cardiovascular death, non-fatal myocardial infarction or non-fatal stroke. The trial was designed as a non-inferiority trial with a pre-specified risk margin of 1.3 for the upper bound of the 95% CI for the hazard ratio of MACE.

The results of CAROLINA, including the contribution of each component to the primary composite endpoint, are shown in Table 13. The Kaplan-Meier curve depicting time to first occurrence of MACE is shown in Figure 3.

Table 13 Major Adverse Cardiovascular Events (MACE) by Treatment Group in the CAROLINA Trial
 | Linagliptin 5 mg n=3,023 |  | Glimepiride (1 mg to 4 mg) n=3,010 |  | Hazard Ratio
 | Number of Subjects (%) | Incidence Rate per 1,000 PY* | Number of Subjects (%) | Incidence Rate per 1,000 PY* | (95% CI)
Composite of first event of CV death, non-fatal myocardial infarction (MI), or non-fatal stroke (MACE) | 356 (11.8) | 20.7 | 362 (12.0) | 21.2 | 0.98 (0.84, 1.14)
CV death** | 169 (5.6) | 9.2 | 168 (5.6) | 9.2 | 1.00 (0.81, 1.24)
Non-fatal MI** | 145 (4.8) | 8.3 | 142 (4.7) | 8.2 | 1.01 (0.80, 1.28)
Non-fatal stroke** | 91 (3.0) | 5.2 | 104 (3.5) | 6.0 | 0.87 (0.66, 1.15)
*PY=patient years
**A patient may have experienced more than one component; therefore, the sum of the components is larger than the number of patients who experienced the composite outcome

Figure 3 Time to First Occurrence of 3P-MACE in CAROLINA

16 HOW SUPPLIED/STORAGE AND HANDLING

JENTADUETO XR (linagliptin and metformin HCl extended-release) tablets 5 mg/1,000 mg, white, oval-shaped coated tablets with one side printed in black ink with the Boehringer Ingelheim symbol and "D5" on the top line and "1000 M" on the bottom line, are supplied as follows:

Bottles of 30 (NDC 0597-0275-33)
Bottles of 90 (NDC 0597-0275-81)

JENTADUETO XR (linagliptin and metformin HCl extended-release) tablets 2.5 mg/1,000 mg, yellow, oval-shaped coated tablets with one side printed in black ink with the Boehringer Ingelheim symbol and "D2" on the top line and "1000 M" on the bottom line, are supplied as follows:

Bottles of 60 (NDC 0597-0270-73)
Bottles of 180 (NDC 0597-0270-94)

Storage

Store at 20°C to 25°C (68°F to 77°F); excursions permitted to 15°C to 30°C (59°F to 86°F) [see USP Controlled Room Temperature]. Protect from exposure to high humidity.

17 PATIENT COUNSELING INFORMATION

Advise the patient to read the FDA-approved patient labeling (Medication Guide)

Lactic Acidosis

Inform patients of the risks of lactic acidosis due to metformin, its symptoms, and conditions that predispose to its development. Advise patients to discontinue JENTADUETO XR immediately and to notify their healthcare provider promptly if unexplained hyperventilation, malaise, myalgia, unusual somnolence, or other nonspecific symptoms occur. Counsel patients against excessive alcohol intake and inform patients about importance of regular testing of renal function while receiving JENTADUETO XR. Instruct patients to inform their healthcare provider that they are taking JENTADUETO XR prior to any surgical or radiological procedure, as temporary discontinuation may be required until renal function has been confirmed to be normal [see Warnings and Precautions (5.1)].

Pancreatitis

Inform patients that acute pancreatitis has been reported during use of linagliptin. Inform patients that persistent severe abdominal pain, sometimes radiating to the back, which may or may not be accompanied by vomiting, is the hallmark symptom of acute pancreatitis. Instruct patients to discontinue JENTADUETO XR promptly and contact their healthcare provider if persistent severe abdominal pain occurs [see Warnings and Precautions (5.2)].

Hypoglycemia with Concomitant Use with Insulin and Insulin Secretagogues

Inform patients that the risk of hypoglycemia is increased when JENTADUETO XR is used in combination with an insulin secretagogue (e.g., sulfonylurea) or insulin [see Warnings and Precautions (5.3)].

Hypersensitivity Reactions

Inform patients that serious allergic reactions, such as anaphylaxis, angioedema, and exfoliative skin conditions, have been reported during postmarketing use of linagliptin (one of the components of JENTADUETO XR). If symptoms of allergic reactions (such as rash, skin flaking or peeling, urticaria, swelling of the skin, or swelling of the face, lips, tongue, and throat that may cause difficulty in breathing or swallowing) occur, patients must stop taking JENTADUETO XR and seek medical advice promptly [see Warnings and Precautions (5.4)].

Administration Instructions

Inform patients taking JENTADUETO XR that the tablets must be swallowed whole and never split, crushed, dissolved, or chewed and that incompletely dissolved JENTADUETO XR tablets may be eliminated in the feces.

Vitamin B12 Deficiency

Inform patients about the importance of regular hematological parameters while receiving JENTADUETO XR [see Warnings and Precautions (5.5)].

Severe and Disabling Arthralgia

Inform patients that severe and disabling joint pain may occur with this class of drugs. The time to onset of symptoms can range from one day to years. Instruct patients to seek medical advice if severe joint pain occurs [see Warnings and Precautions (5.6)].

Bullous Pemphigoid

Inform patients that bullous pemphigoid has been reported during use of linagliptin. Instruct patients to seek medical advice if blisters or erosions occur [see Warnings and Precautions (5.7)].

Heart Failure

Inform patients of the signs and symptoms of heart failure. Before initiating JENTADUETO XR, patients should be asked about a history of heart failure or other risk factors for heart failure including moderate to severe renal impairment. Instruct patients to contact their healthcare provider as soon as possible if they experience symptoms of heart failure, including increasing shortness of breath, rapid increase in weight or swelling of the feet [see Warnings and Precautions (5.8)].

Patients of Reproductive Potential

Inform patients that treatment with metformin may result in ovulation in some premenopausal anovulatory patients, which may lead to unintended pregnancy [see Use in Specific Populations (8.3)].

Missed Dose

Instruct patients to take JENTADUETO XR only as prescribed. If a dose is missed, it should be taken as soon as the patient remembers. Advise patients not to double their next dose.

Distributed by:
Boehringer Ingelheim Pharmaceuticals, Inc.
Ridgefield, CT 06877 USA

Licensed from:
Boehringer Ingelheim International GmbH, Ingelheim, Germany

JENTADUETO is a registered trademark of and used under license from Boehringer Ingelheim International GmbH.

Boehringer Ingelheim Pharmaceuticals, Inc. either owns or uses the Tradjenta®, CARMELINA®, and CAROLINA® trademarks under license.

The other brands listed are trademarks of their respective owners and are not trademarks of Boehringer Ingelheim Pharmaceuticals, Inc.

Copyright © 2023 Boehringer Ingelheim International GmbH
ALL RIGHTS RESERVED

COL9394FF212023

SPL9396B

MEDICATION GUIDE
JENTADUETO® XR (JEN ta doo e toe XR)
(linagliptin and metformin hydrochloride extended-release tablets)
for oral use

What is the most important information I should know about JENTADUETO XR?
JENTADUETO XR can cause serious side effects, including:

1.

Lactic acidosis. Metformin hydrochloride (HCl), one of the medicines in JENTADUETO XR, can cause a rare but serious condition called lactic acidosis (a build-up of lactic acid in the blood) that can cause death. Lactic acidosis is a medical emergency and must be treated in a hospital.
Stop taking JENTADUETO XR and call your healthcare provider right away or go to the nearest hospital emergency room if you get any of the following symptoms of lactic acidosis:

- feel very weak and tired
- have unusual (not normal) muscle pain
- have trouble breathing
- have unexplained stomach or intestinal problems with nausea and vomiting, or diarrhea

- have unusual sleepiness or sleep longer than usual
- feel cold, especially in your arms and legs
- feel dizzy or lightheaded
- have a slow or irregular heartbeat

You have a higher chance of getting lactic acidosis with JENTADUETO XR if you:

- have severe kidney problems.
- have liver problems.
- drink a lot of alcohol (very often or short-term "binge" drinking).
- get dehydrated (lose a large amount of body fluids). This can happen if you are sick with a fever, vomiting, or diarrhea. Dehydration can also happen when you sweat a lot with activity or exercise and do not drink enough fluids.
- have certain x-ray tests with injectable dyes or contrast agents.
- have surgery or other procedures for which you need to restrict the amount of food and liquid you eat and drink.
- have congestive heart failure.
- have a heart attack, severe infection, or stroke.
- are 65 years of age or older.

Tell your healthcare provider if you have any of the problems in the list above. Tell your healthcare provider that you are taking JENTADUETO XR before you have surgery or x-ray tests. Your healthcare provider may decide to stop your JENTADUETO XR for a while if you have surgery or certain x-ray tests. JENTADUETO XR can have other serious side effects. See "What are the possible side effects of JENTADUETO XR?"

2.

Inflammation of the pancreas (pancreatitis) which may be severe and lead to death. Certain medical problems make you more likely to get pancreatitis.
Before you start taking JENTADUETO XR, tell your healthcare provider if you have ever had:

- inflammation of your pancreas (pancreatitis)
- a history of alcoholism

- stones in your gallbladder (gallstones)
- high blood triglyceride levels

Stop taking JENTADUETO XR and call your healthcare provider right away if you have pain in your stomach area (abdomen) that is severe and will not go away. The pain may be felt going from your abdomen to your back. The pain may happen with or without vomiting. These may be symptoms of pancreatitis.

What is JENTADUETO XR?

- JENTADUETO XR is a prescription medicine that contains 2 diabetes medicines, linagliptin (TRADJENTA) and metformin HCl. JENTADUETO XR can be used along with diet and exercise to lower blood sugar in adults with type 2 diabetes mellitus.
- JENTADUETO XR is not for people with type 1 diabetes mellitus.
- If you have had pancreatitis in the past, it is not known if you have a higher chance of getting pancreatitis while you take JENTADUETO XR.
- It is not known if JENTADUETO XR is safe and effective in children.

Who should not take JENTADUETO XR?
Do not take JENTADUETO XR if you:

- have severe kidney problems.
- have a condition called metabolic acidosis or diabetic ketoacidosis (increased ketones in the blood or urine).
- are allergic to linagliptin (TRADJENTA), metformin, or any of the ingredients in JENTADUETO XR. See the end of this Medication Guide for a complete list of ingredients in JENTADUETO XR.
  Symptoms of a serious allergic reaction to JENTADUETO XR may include:
  - skin rash, itching, flaking or peeling
  - raised red patches on your skin (hives)
  - swelling of your face, lips, tongue and throat that may cause difficulty in breathing or swallowing
  - difficulty with swallowing or breathing

If you have any of these symptoms, stop taking JENTADUETO XR and call your healthcare provider right away or go to the nearest hospital emergency room.

What should I tell my healthcare provider before taking JENTADUETO XR?
Before taking JENTADUETO XR, tell your healthcare provider about all of your medical conditions, including if you:

- have or have had inflammation of your pancreas (pancreatitis).
- have kidney problems.
- have liver problems.
- have heart problems, including congestive heart failure.
- are 65 years of age or older.
- drink alcohol very often, or drink a lot of alcohol in short term ("binge" drinking).
- are going to get an injection of dye or contrast agents for an x-ray procedure. JENTADUETO XR may need to be stopped for a short time. Talk to your healthcare provider about when you should stop JENTADUETO XR and when you should start JENTADUETO XR again. See "What is the most important information I should know about JENTADUETO XR?"
- have type 1 diabetes mellitus. JENTADUETO XR should not be used to treat people with type 1 diabetes mellitus.
- have low levels of vitamin B12 in your blood.
- are pregnant or plan to become pregnant. It is not known if JENTADUETO XR will harm your unborn baby. If you are pregnant, talk with your healthcare provider about the best way to control your blood sugar while you are pregnant.
- are breastfeeding or plan to breastfeed. JENTADUETO XR may pass into your breast milk and may harm your baby. Talk with your healthcare provider about the best way to feed your baby if you take JENTADUETO XR.
- are a person who has not gone through menopause (premenopausal) who does not have periods regularly or at all. JENTADUETO XR can cause the release of an egg from an ovary in a person (ovulation). This can increase your chance of getting pregnant. Tell your healthcare provider right away if you become pregnant while taking JENTADUETO XR.

Tell your healthcare provider about all the medicines you take, including prescription and over-the-counter medicines, vitamins, and herbal supplements.
JENTADUETO XR may affect the way other medicines work, and other medicines may affect how JENTADUETO XR works.
Know the medicines you take. Keep a list of them to show your healthcare provider and pharmacist when you get a new medicine.

How should I take JENTADUETO XR?

- Take JENTADUETO XR exactly as your healthcare provider tells you to take it.
- Take JENTADUETO XR 1 time each day with a meal. Taking JENTADUETO XR with a meal may lower your chance of having an upset stomach.
- Swallow JENTADUETO XR tablets whole. Do not break, cut, crush, dissolve, or chew JENTADUETO XR tablets. If you cannot swallow JENTADUETO XR tablets whole, tell your healthcare provider.
- You may see something that looks like the JENTADUETO XR tablet in your stool (bowel movement). This is not harmful and should not affect the way JENTADUETO XR works to control your diabetes.
- If you miss a dose, take it with food as soon as you remember. If you do not remember until it is time for your next dose, skip the missed dose and go back to your regular schedule. Do not take 2 doses of JENTADUETO XR at the same time.
- If you take too much JENTADUETO XR, call your healthcare provider or local poison control center or go to the nearest hospital emergency room right away.
- Your healthcare provider may tell you to take JENTADUETO XR along with other diabetes medicines. Low blood sugar can happen more often when JENTADUETO XR is taken with certain other diabetes medicines. See "What are the possible side effects of JENTADUETO XR?"
- Your healthcare provider will do blood tests to check how well your kidneys are working before and during your treatment with JENTADUETO XR.

What should I avoid while taking JENTADUETO XR?
Avoid drinking alcohol very often or drinking a lot of alcohol in a short period of time ("binge" drinking). It can increase your chances of getting serious side effects.

What are the possible side effects of JENTADUETO XR?
JENTADUETO XR may cause serious side effects, including:

- See "What is the most important information I should know about JENTADUETO XR?"
- Low blood sugar (hypoglycemia). If you take JENTADUETO XR with another medicine that can cause low blood sugar, such as a sulfonylurea or insulin, your risk of getting low blood sugar is higher. The dose of your sulfonylurea medicine or insulin may need to be lowered while you take JENTADUETO XR. Signs and symptoms of low blood sugar may include:

- headache
- fast heartbeat

- irritability
- dizziness

- drowsiness
- sweating

- hunger
- confusion

- weakness
- shaking or feeling jittery

- Allergic (hypersensitivity) reactions. Serious allergic reactions have happened in people who are taking JENTADUETO XR. Symptoms may include:

- swelling of your face, lips, tongue, throat, and other areas on your skin
- raised, red areas on your skin (hives)

- difficulty with swallowing or breathing
- skin rash, itching, flaking, or peeling

If you have any of these symptoms, stop taking JENTADUETO XR and call your healthcare provider right away or go to the nearest hospital emergency room.

- Low vitamin B12 (vitamin B12 deficiency). Using metformin for long periods of time may cause a decrease in the amount of vitamin B12 in your blood, especially if you have had low vitamin B12 blood levels before. Your healthcare provider may do blood tests to check your vitamin B12 levels.
- Joint pain. Some people who take linagliptin, one of the medicines in JENTADUETO XR, may develop joint pain that can be severe. Call your healthcare provider if you have severe joint pain.
- Skin reaction. Some people who take medicines called DPP-4 inhibitors, one of the medicines in JENTADUETO XR, may develop a skin reaction called bullous pemphigoid that can require treatment in a hospital. Tell your healthcare provider right away if you develop blisters or the breakdown of the outer layer of your skin (erosion). Your healthcare provider may tell you to stop taking JENTADUETO XR.
- Heart failure. Heart failure means your heart does not pump blood well enough.
  Before you start taking JENTADUETO XR, tell your healthcare provider if you have ever had heart failure or have problems with your kidneys. Contact your healthcare provider right away if you have any of the following symptoms:
  - increasing shortness of breath or trouble breathing, especially when you lie down
  - swelling or fluid retention, especially in the feet, ankles or legs
  - an unusually fast increase in weight
  - unusual tiredness
  These may be symptoms of heart failure.

The most common side effects of JENTADUETO XR include:

- stuffy or runny nose and sore throat
- diarrhea.

Tell your healthcare provider if you have any side effects that bother you or that do not go away.
These are not all the possible side effects of JENTADUETO XR. For more information, ask your healthcare provider or pharmacist.
Call your doctor for medical advice about side effects. You may report side effects to FDA at 1-800-FDA-1088.

How should I store JENTADUETO XR?

- Store JENTADUETO XR at room temperature between 68°F and 77°F (20°C and 25°C).
- Keep tablets dry.

Keep JENTADUETO XR and all medicines out of the reach of children.

General information about the safe and effective use of JENTADUETO XR.
Medicines are sometimes prescribed for purposes other than those listed in a Medication Guide. Do not use JENTADUETO XR for a condition for which it was not prescribed. Do not give JENTADUETO XR to other people, even if they have the same symptoms you have. It may harm them.
You can ask your pharmacist or healthcare provider for information about JENTADUETO XR that is written for health professionals.

What are the ingredients in JENTADUETO XR?
Active Ingredients: linagliptin and metformin HCl
Inactive Ingredients: hypromellose, magnesium stearate, and polyethylene oxide. The coating contains the following inactive ingredients: arginine, carnauba wax, ferric oxide yellow (2.5 mg/1,000 mg), ferrosoferric oxide, hydroxypropyl cellulose, hypromellose, isopropyl alcohol, polyethylene glycol, propylene glycol, talc, and titanium dioxide.

Distributed by: Boehringer Ingelheim Pharmaceuticals, Inc. Ridgefield, CT 06877 USA.
Licensed from: Boehringer Ingelheim International GmbH, Ingelheim, Germany.
JENTADUETO is a registered trademark of and used under license from Boehringer Ingelheim International GmbH.
Boehringer Ingelheim Pharmaceuticals, Inc. either owns or uses the Tradjenta®, CARMELINA®, and CAROLINA® trademarks under license.
The other brands listed are trademarks of their respective owners and are not trademarks of Boehringer Ingelheim Pharmaceuticals, Inc.
Copyright © 2023 Boehringer Ingelheim International GmbH
ALL RIGHTS RESERVED
COL9394FF212023
For more information about JENTADUETO XR, including current prescribing information and Medication Guide, go to www.JENTADUETOXR.com, scan the code, or call Boehringer Ingelheim Pharmaceuticals, Inc. at 1-800-542-6257.

This Medication Guide has been approved by the U.S. Food and Drug Administration

Revised: June 2023

PRINCIPAL DISPLAY PANEL - 2.5 mg/1,000 mg Tablet Bottle Label

NDC 0597-0270-73

DISPENSE WITH ACCOMPANYING MEDICATION GUIDE

Jentadueto® XR
(linagliptin and metformin
hydrochloride extended-release tablets)

2.5 mg/1,000 mg*

Rx only

60 tablets

Boehringer
Ingelheim

PRINCIPAL DISPLAY PANEL - 5 mg/1,000 mg Tablet Bottle Label

NDC 0597-0275-33

DISPENSE WITH ACCOMPANYING
MEDICATION GUIDE

Jentadueto® XR
(linagliptin and metformin
hydrochloride extended-release
tablets)

5 mg/1,000 mg*

Rx only

30 tablets

Boehringer
Ingelheim